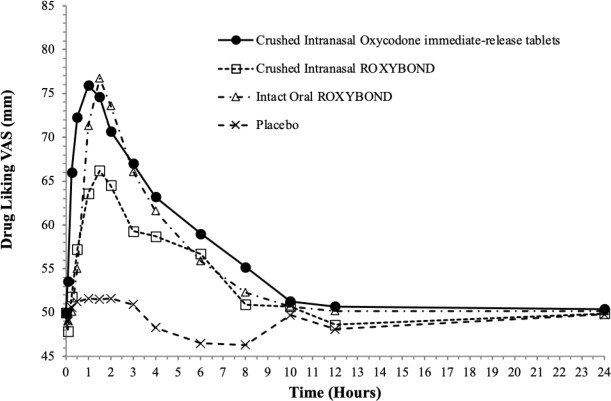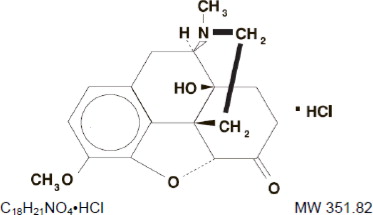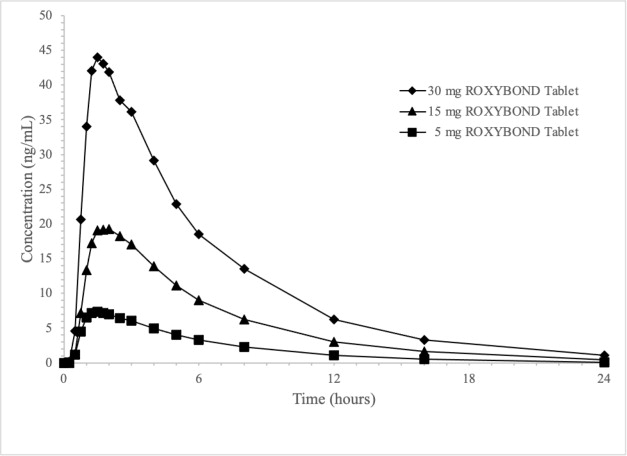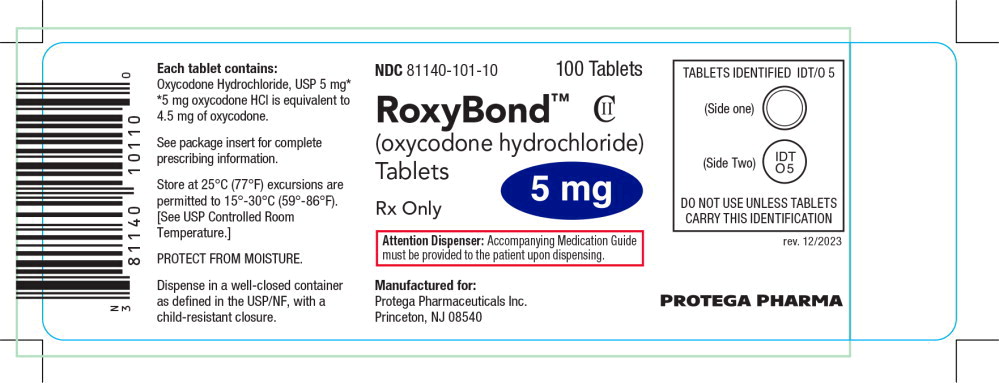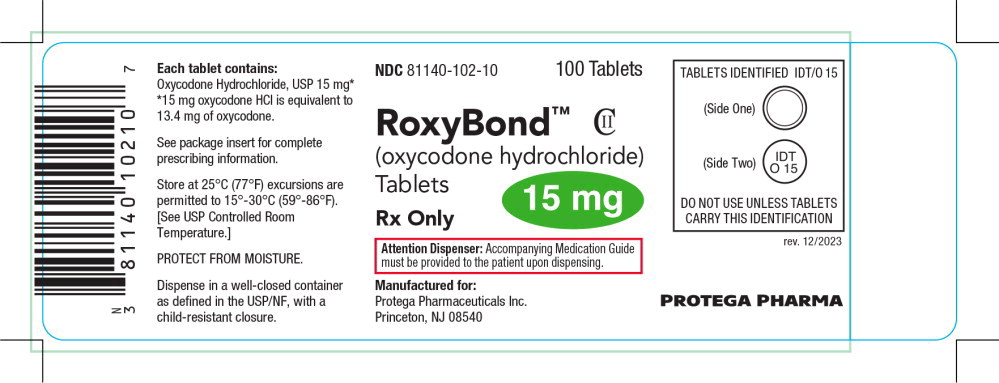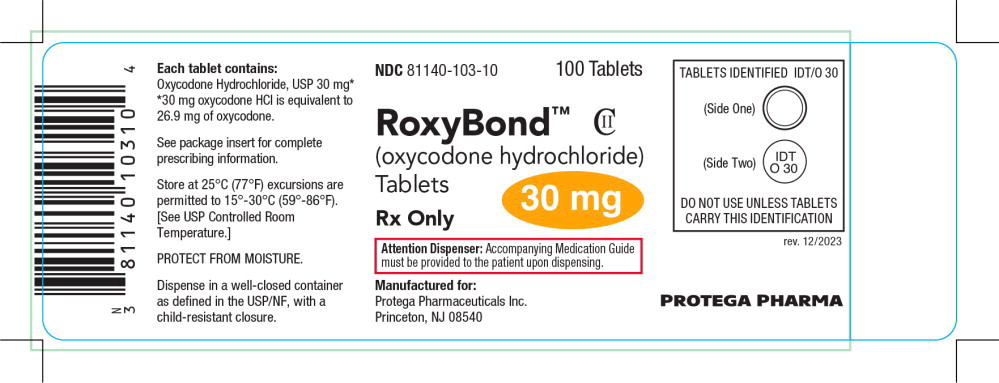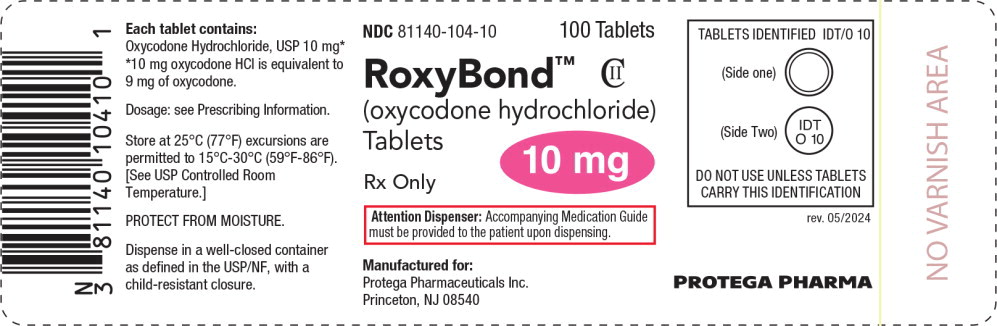 DRUG LABEL: RoxyBond
NDC: 81140-101 | Form: TABLET, COATED
Manufacturer: Protega Pharmaceuticals Inc
Category: prescription | Type: HUMAN PRESCRIPTION DRUG LABEL
Date: 20260113
DEA Schedule: CII

ACTIVE INGREDIENTS: OXYCODONE HYDROCHLORIDE 5 mg/1 1
INACTIVE INGREDIENTS: ALGINIC ACID; AMMONIA; SILICON DIOXIDE; DIBUTYL SEBACATE; DIMETHYLAMINOETHYL METHACRYLATE - BUTYL METHACRYLATE - METHYL METHACRYLATE COPOLYMER; ETHYL ACRYLATE AND METHYL METHACRYLATE COPOLYMER DISPERSION (2:1; 750000 MW 40% AQUEOUS); ETHYLCELLULOSE (45 MPA.S); HYPROMELLOSE 2208 (4000 MPA.S); FERROSOFERRIC OXIDE; ISOPROPYL ALCOHOL; LACTOSE MONOHYDRATE; MAGNESIUM STEARATE; MANNITOL; MICROCRYSTALLINE CELLULOSE; BUTYL ALCOHOL; POLYETHYLENE GLYCOL, UNSPECIFIED; POLYSORBATE 80; POLYVINYL ALCOHOL, UNSPECIFIED; PROPYLENE GLYCOL; SHELLAC; SODIUM ALGINATE; TALC; TITANIUM DIOXIDE; XANTHAN GUM

HIGHLIGHTS OF PRESCRIBING INFORMATION

These highlights do not include all the information needed to use ROXYBOND™ safely and effectively. See full prescribing information for ROXYBOND.
ROXYBOND (oxycodone hydrochloride) tablets, for oral use, CII
Initial U.S. Approval: 1950

RECENT MAJOR CHANGES

Boxed Warning | 12/2025
Indications and Usage (1) | 12/2025
Dosage and Administration (2.2, 2.5) | 12/2025
Warnings and Precautions (5.1, 5.2, 5.3, 5.12, 5.14) | 12/2025

WARNING: SERIOUS AND LIFE-THREATENING RISKS FROM USE OF ROXYBOND

See full prescribing information for complete boxed warning.

- ROXYBOND exposes users to risks of addiction, abuse, and misuse, which can lead to overdose and death. Assess patient's risk before prescribing and reassess regularly for these behaviors and conditions. (5.1)
- Serious, life-threatening, or fatal respiratory depression may occur, especially during initiation or following a dosage increase. To reduce the risk of respiratory depression, proper dosing and titration of ROXYBOND are essential. (5.2)
- Accidental ingestion of ROXYBOND, especially by children, can result in a fatal overdose of oxycodone. (5.2)
- Concomitant use of opioids with benzodiazepines or other central nervous system (CNS) depressants, including alcohol, may result in profound sedation, respiratory depression, coma, and death. Reserve concomitant prescribing for use in patients for whom alternative treatment options are inadequate. (5.3, 7)
- Advise pregnant women using opioids for an extended period of time of the risk of Neonatal Opioid Withdrawal Syndrome, which may be life-threatening if not recognized and treated. Ensure that management by neonatology experts will be available at delivery. (5.4)
- Healthcare providers are strongly encouraged to complete a REMS-compliant education program and to counsel patients and caregivers on serious risks, safe use, and the importance of reading the Medication Guide with each prescription. (5.5)
- Concomitant use with CYP3A4 inhibitors (or discontinuation of CYP3A4 inducers) can result in a fatal overdose of oxycodone. (5.6, 7, 12.3)

1 INDICATIONS AND USAGE

ROXYBOND is an opioid agonist indicated for the management of pain severe enough to require an opioid analgesic and for which alternative treatments are inadequate. (1)

Limitations of Use

Because of the risks of addiction, abuse, misuse, overdose, and death, which can occur at any dosage or duration and persist over the course of therapy, reserve opioid analgesics, including ROXYBOND, for use in patients for whom alternative treatment options are ineffective, not tolerated, or would be otherwise inadequate to provide sufficient management of pain. (1, 5.1)

2 DOSAGE AND ADMINISTRATION

- ROXYBOND should be prescribed only by healthcare professionals who are knowledgeable about the use of opioids and how to mitigate the associated risks. (2.1)
- Use the lowest effective dosage for the shortest duration of time consistent with individual patient treatment goals. Reserve titration to higher doses of ROXYBOND for patients in whom lower doses are insufficiently effective and in whom the expected benefits of using a higher dose opioid clearly outweigh the substantial risks. (2.1, 5)
- Many acute pain conditions (e.g., the pain that occurs with a number of surgical procedures or acute musculoskeletal injuries) require no more than a few days of an opioid analgesic. Clinical guidelines on opioid prescribing for some acute pain conditions are available. (2.1)
- Initiate the dosing regimen for each patient individually, taking into account the patient's underlying cause and severity of pain, prior analgesic treatment and response, and risk factors for addiction, abuse, and misuse. (2.1, 5.1)
- Respiratory depression can occur at any time during opioid therapy, especially when initiating and following dosage increases with ROXYBOND. Consider this risk when selecting an initial dose and when making dose adjustments. (2.1, 5.2)
- Discuss opioid overdose reversal agents and options for acquiring them with the patient and/or caregiver, both when initiating and renewing treatment with ROXYBOND, especially if the patient has additional risk factors for overdose, or close contacts at risk for exposure and overdose. (2.2, 5.1, 5.2, 5.3)
- Initiate dosing with a range of 5 to 15 mg every 4 to 6 hours as needed for pain, and at the lowest dose necessary to achieve adequate analgesia. Titrate the dose based upon the individual patient's response to their initial dose of ROXYBOND. (2.3, 2.4)
- Periodically reassess patients receiving ROXYBOND to evaluate the continued need for opioid analgesics to maintain pain control, for the signs or symptoms of adverse reactions, and for the development of addiction, abuse, or misuse. (2.4, 5.1, 5.14, 6)
- Do not rapidly reduce or abruptly discontinue ROXYBOND in a physically dependent patient because rapid reduction or abrupt discontinuation of opioid analgesics has resulted in serious withdrawal symptoms, uncontrolled pain, and suicide. (2.4, 5.14, 9.3)

3 DOSAGE FORMS AND STRENGTHS

Tablets: 5 mg, 10 mg, 15 mg, 30 mg (3)

4 CONTRAINDICATIONS

- Significant respiratory depression (4)
- Acute or severe bronchial asthma in an unmonitored setting or in absence of resuscitative equipment (4)
- Known or suspected gastrointestinal obstruction, including paralytic ileus (4)
- Hypersensitivity to oxycodone (4)

5 WARNINGS AND PRECAUTIONS

- Opioid-Induced Hyperalgesia and Allodynia: Opioid-Induced Hyperalgesia (OIH) occurs when an opioid analgesic paradoxically causes an increase in pain, or an increase in sensitivity to pain. If OIH is suspected, carefully consider appropriately decreasing the dose of the current opioid analgesic, or opioid rotation. (5.7)
- Life-Threatening Respiratory Depression in Patients with Chronic Pulmonary Disease or in Elderly, Cachectic, or Debilitated Patients: Regularly evaluate, particularly during initiation and titration. (5.8)
- Adrenal Insufficiency: If diagnosed, treat with physiologic replacement of corticosteroids, and wean patient off of the opioid. (5.9)
- Severe Hypotension: Regularly evaluate during dosage initiation and titration. Avoid use of ROXYBOND in patients with circulatory shock. (5.10)
- Risks of Use in Patients with Increased Intracranial Pressure, Brain Tumors, Head Injury, or Impaired Consciousness: Monitor for sedation and respiratory depression. Avoid use of ROXYBOND in patients with impaired consciousness or coma. (5.11)

6 ADVERSE REACTIONS

Most common adverse reactions (≥3%): nausea, constipation, vomiting, headache, pruritus, insomnia, dizziness, asthenia, and somnolence. (6.1)

To report SUSPECTED ADVERSE REACTIONS, contact Protega Pharmaceuticals Inc. at 1-844-798-3610 or FDA at 1-800-FDA-1088 or www.fda.gov/medwatch.

7 DRUG INTERACTIONS

- Serotonergic Drugs: Concomitant use may result in serotonin syndrome. Discontinue ROXYBOND if serotonin syndrome is suspected. (7)
- Mixed Agonist/Antagonist and Partial Agonist Opioid Analgesics:Avoid use with ROXYBOND because they may reduce analgesic effect of ROXYBOND or precipitate withdrawal symptoms. (7)
- Monoamine Oxidase Inhibitors (MAOIs):Can potentiate the effects of morphine. Avoid concomitant use in patients receiving MAOIs or within 14 days of stopping treatment with an MAOI. (7)

8 USE IN SPECIFIC POPULATIONS

Pregnancy: May cause fetal harm. (8.1)

FULL PRESCRIBING INFORMATION

WARNING: SERIOUS AND LIFE-THREATENING RISKS FROM USE OF ROXYBOND

Addiction, Abuse, and Misuse

Because the use of ROXYBOND exposes patients and other users to the risks of opioid addiction, abuse, and misuse, which can lead to overdose and death, assess each patient's risk prior to prescribing and reassess all patients regularly for the development of these behaviors and conditions [see Warnings and Precautions (5.1)] .

Life-Threatening Respiratory Depression

Serious, life-threatening, or fatal respiratory depression may occur with use of ROXYBOND, especially during initiation or following a dosage increase. To reduce the risk of respiratory depression, proper dosing and titration of ROXYBOND are essential [see Warnings and Precautions (5.2)] .

Accidental Ingestion

Accidental ingestion of even one dose of ROXYBOND, especially by children, can result in a fatal overdose of oxycodone [see Warnings and Precautions (5.2)] .

Risks From Concomitant Use With Benzodiazepines Or Other CNS Depressants

Concomitant use of opioids with benzodiazepines or other central nervous system (CNS) depressants, including alcohol, may result in profound sedation, respiratory depression, coma, and death. Reserve concomitant prescribing of ROXYBOND and benzodiazepines or other CNS depressants for use in patients for whom alternative treatment options are inadequate [see Warnings and Precautions (5.3), Drug Interactions (7)].

Neonatal Opioid Withdrawal Syndrome (NOWS)

Advise pregnant women using opioids for an extended period of time of the risk of Neonatal Opioid Withdrawal Syndrome, which may be life-threatening if not recognized and treated. Ensure that management by neonatology experts will be available at delivery [see Warnings and Precautions (5.4)] .

Opioid Analgesic Risk Evaluation and Mitigation Strategy (REMS)

Healthcare providers are strongly encouraged to complete a REMS-compliant education program and to counsel patients and caregivers on serious risks, safe use, and the importance of reading the Medication Guide with each prescription [see Warnings and Precautions (5.5)] .

Cytochrome P450 3A4 Interaction

The concomitant use of ROXYBOND with all cytochrome P450 3A4 inhibitors may result in an increase in oxycodone plasma concentrations, which could increase or prolong adverse reactions and may cause potentially fatal respiratory depression. In addition, discontinuation of a concomitantly used cytochrome P450 3A4 inducer may result in an increase in oxycodone plasma concentration. Regularly evaluate patients receiving ROXYBOND and any CYP3A4 inhibitor or inducer [see Warnings and Precautions (5.6), Drug Interactions (7), Clinical Pharmacology (12.3)] .

1 INDICATIONS AND USAGE

ROXYBOND is indicated for the management of pain severe enough to require an opioid analgesic and for which alternative treatments are inadequate.

Limitations of Use

Because of the risks of addiction, abuse, misuse, overdose, and death, which can occur any dosage or duration and persist over the course of therapy, [see Warnings and Precautions (5.1)] , reserve opioid analgesics, including ROXYBOND, for use in patients for whom alternative treatment options are ineffective, not tolerated, or would be otherwise inadequate to provide sufficient management of pain.

2 DOSAGE AND ADMINISTRATION

2.1 Important Dosage and Administration Instructions

- ROXYBOND should be prescribed only by healthcare professionals who are knowledgeable about the use of opioids and how to mitigate the associated risks.
- Use the lowest effective dosage for the shortest duration of time consistent with individual patient treatment goals. Because the risk of overdose increases as opioid doses increase, reserve titration to higher doses of ROXYBOND for patients in whom lower doses are insufficiently effective and in whom the expected benefits of using a higher dose opioid clearly outweigh the substantial risks [see Warnings and Precautions (5)] .
- Many acute pain conditions (e.g., the pain that occurs with a number of surgical procedures or acute musculoskeletal injuries) require no more than a few days of an opioid analgesic. Clinical guidelines on opioid prescribing for some acute pain conditions are available.
- There is variability in the opioid analgesic dose and duration needed to adequately manage pain due both to the cause of pain and to individual patient factors. Initiate the dosing regimen for each patient individually, taking into account the patient's underlying cause and severity of pain, prior analgesic treatment and response, and risk factors for addiction, abuse, and misuse [see Warnings and Precautions (5.1)] .
- Respiratory depression can occur at any time during opioid therapy, especially when initiating and following dosage increases with ROXYBOND. Consider this risk when selecting an initial dose and when making dose adjustments [see Warnings and Precautions (5.2)] .

2.2 Patient Access to an Opioid Overdose Reversal Agent for the Emergency Treatment of Opioid Overdose

Inform patients and caregivers about opioid overdose reversal agents (e.g., naloxone, nalmefene). Discuss the importance of having access to an opioid overdose reversal agent, especially if the patient has risk factors for overdose (e.g., concomitant use of CNS depressants, a history of opioid use disorder, or prior opioid overdose) or if there are household members (including children) or other close contacts at risk for accidental ingestion or opioid overdose. The presence of risk factors for overdose should not prevent the management of pain in any patient [see Warnings and Precautions (5.1, 5.2, 5.3)] .

Discuss the options for obtaining an opioid overdose reversal agent (e.g., prescription, over-the-counter, or as part of a community-based program) [see Warnings and Precautions (5.2)] .

There are important differences among the opioid overdose reversal agents, such as route of administration, product strength, approved patient age range, and pharmacokinetics. Be familiar with these differences, as outlined in the approved labeling for those products, prior to recommending or prescribing such an agent.

2.3 Initial Dosage

Use of ROXYBOND as the First Opioid Analgesic

Initiate treatment with ROXYBOND in a dosing range of 5 to 15 mg every 4 to 6 hours as needed for pain, and at the lowest dose necessary to achieve adequate analgesia. Titrate the dose based upon the individual patient's response to their initial dose of ROXYBOND.

Although it is not possible to list every condition that is important to the selection of the initial dose of ROXYBOND, attention should be given to: 1) the daily dose, potency, and characteristics of any prior opioid 2) the reliability of any relative potency estimate used to calculate the dose of oxycodone needed, 3) the degree of opioid tolerance, 4) the general condition and medical status of the patient, and 5) the balance between pain control and adverse experiences.

Conversion from Other Opioids to ROXYBOND

There is inter-patient variability in the potency of opioid drugs and opioid formulations. Therefore, a conservative approach is advised when determining the total daily dosage of ROXYBOND. It is safer to underestimate a patient's 24-hour ROXYBOND dosage than to overestimate the 24-hour ROXYBOND dosage and manage an adverse reaction due to overdose. If a patient has been receiving opioid-containing medications prior to taking ROXYBOND, the potency of the prior opioid relative to oxycodone should be factored into the selection of the total daily dose (TDD) of oxycodone.

In converting patients from other opioids to ROXYBOND, close observation and adjustment of dosage based upon the patient's response to ROXYBOND is imperative. Administration of supplemental analgesia for breakthrough or incident pain and titration of the TDD of ROXYBOND may be necessary, especially in patients who have disease states that are changing rapidly.

Conversion From Fixed-Ratio Opioid/Acetaminophen, Opioid/Aspirin, or Opioid/Nonsteroidal Combination Drugs

When converting patients from fixed ratio opioid/non-opioid drug regimens, a decision should be made whether or not to continue the non-opioid analgesic. If a decision is made to discontinue the use of non-opioid analgesic, it may be necessary to titrate the dose of ROXYBOND in response to the level of analgesia and adverse effects afforded by the dosing regimen. If the non-opioid regimen is continued as a separate single entity agent, the starting dose of ROXYBOND should be based upon the most recent dose of opioid as a baseline for further titration of oxycodone. Incremental increases should be gauged according to side effects to an acceptable level of analgesia.

Conversion from ROXYBOND to Extended-Release Oxycodone

The relative bioavailability of ROXYBOND compared to extended-release oxycodone products is unknown, so conversion to extended-release oxycodone may lead to increased risk of excessive sedation and respiratory depression.

Conversion from Oxycodone Immediate-Release Tablets

Oxycodone pharmacokinetics are similar for ROXYBOND and oxycodone immediate-release tablets. Patients can be converted from oxycodone immediate-release to the same dose and dosing regimen of ROXYBOND.

2.4 Titration and Maintenance of Therapy

Individually titrate ROXYBOND to a dose that provides adequate analgesia and minimizes adverse reactions. Continually reevaluate patients receiving ROXYBOND to assess the maintenance of pain control, signs and symptoms of opioid withdrawal, and other adverse reactions, as well as reassess for the development of addiction, abuse, or misuse [see Warnings and Precautions (5.1, 5.14)] . Frequent communication is important among the prescriber, other members of the healthcare team, the patient, and the caregiver/family during periods of changing analgesic requirements, including initial titration.

If the level of pain increases after dosage stabilization, attempt to identify the source of increased pain before increasing the ROXYBOND dosage. If after increasing the dosage, unacceptable opioid-related adverse reactions are observed (including an increase in pain after dosage increase), consider reducing the dosage [see Warnings and Precautions (5)] . Adjust the dosage to obtain an appropriate balance between management of pain and opioid-related adverse reactions.

2.5 Safe Reduction or Discontinuation of ROXYBOND

Do not rapidly reduce or abruptly discontinue ROXYBOND in patients who may be physically dependent on opioids. Rapid reduction or discontinuation of opioid analgesics in patients who are physically dependent on opioids has resulted in serious withdrawal symptoms, uncontrolled pain, and suicide. Rapid reduction or abrupt discontinuation has also been associated with attempts to find other sources of opioid analgesics, which may be confused with drug-seeking for abuse. Patients may also attempt to treat their pain or withdrawal symptoms with illicit opioids, such as heroin, and other substances.

When a decision has been made to decrease the dose or discontinue therapy in an opioid-dependent patient taking ROXYBOND, there are a variety of factors that should be considered, including the total daily dose of opioid (including ROXYBOND) the patient has been taking, the duration of treatment, the type of pain being treated, and the physical and psychological attributes of the patient. It is important to ensure ongoing care of the patient and to agree on an appropriate tapering schedule and follow-up plan so that patient and provider goals and expectations are clear and realistic. When opioid analgesics are being discontinued due to a suspected substance use disorder, evaluate and treat the patient, or refer for evaluation and treatment of the substance use disorder. Treatment should include evidence-based approaches, such as medication assisted treatment of opioid use disorder. Complex patients with comorbid pain and substance use disorders may benefit from referral to a specialist.

There are no standard opioid tapering schedules that are suitable for all patients. Good clinical practice dictates a patient-specific plan to taper the dose of the opioid gradually. For patients on ROXYBOND who are physically opioid-dependent, initiate the taper by a small enough increment (e.g., no greater than 10% to 25% of the total daily dose) to avoid withdrawal symptoms, and proceed with dose-lowering at an interval of every 2 to 4 weeks. Patients who have been taking opioids for briefer periods of time may tolerate a more rapid taper.

It may be necessary to provide the patient with lower dosage strengths to accomplish a successful taper. Reassess the patient frequently to manage pain and withdrawal symptoms, should they emerge. Common withdrawal symptoms include restlessness, lacrimation, rhinorrhea, yawning, perspiration, chills, myalgia, and mydriasis. Other signs and symptoms also may develop, including irritability, anxiety, backache, joint pain, weakness, abdominal cramps, insomnia, nausea, anorexia, vomiting, diarrhea, or increased blood pressure, respiratory rate, or heart rate. If withdrawal symptoms arise, it may be necessary to pause the taper for a period of time or raise the dose of the opioid analgesic to the previous dose, and then proceed with a slower taper. In addition, evaluate patients for any changes in mood, emergence of suicidal thoughts, or use of other substances.

When managing patients taking opioid analgesics, particularly those who have been treated for an extended period of time, and/or with high doses for chronic pain, ensure that a multimodal approach to pain management, including mental health support (if needed), is in place prior to initiating an opioid analgesic taper. A multimodal approach to pain management may optimize the treatment of chronic pain, as well as assist with the successful tapering of the opioid analgesic [see Warnings and Precautions (5.14), Drug Abuse and Dependence (9.3)] .

3 DOSAGE FORMS AND STRENGTHS

ROXYBOND (oxycodone hydrochloride) tablets, 5 mg, 10 mg, 15 mg, and 30 mg with the following characteristics:

Strength | Tablet Shape | Tablet Color | Ink-Print on Tablet Side 1 | Ink-Print on Tablet Side 2
5 mg | Round coated tablets | White | IDT/O 5 | None
10 mg | Round coated tablets | Pink | IDT/O 10 | None
15 mg | Round coated tablets | Green | IDT/O 15 | None
30 mg | Round coated tablets | Blue | IDT/O 30 | None

4 CONTRAINDICATIONS

ROXYBOND is contraindicated in patients with:

- Significant respiratory depression [see Warnings and Precautions (5.2)]
- Acute or severe bronchial asthma in an unmonitored setting or in the absence of resuscitative equipment or hypercarbia [see Warnings and Precautions (5.8)]
- Known or suspected gastrointestinal obstruction, including paralytic ileus [see Warnings and Precautions (5.12)]
- Known hypersensitivity (e.g., anaphylaxis) to oxycodone [see Adverse Reactions (6.2)]

5 WARNINGS AND PRECAUTIONS

5.1 Addiction, Abuse, and Misuse

ROXYBOND contains oxycodone, a Schedule II controlled substance. As an opioid, ROXYBOND exposes users to the risks of addiction, abuse, and misuse [see Drug Abuse and Dependence (9)] .

Although the risk of addiction in any individual is unknown, it can occur in patients appropriately prescribed ROXYBOND. Addiction can occur at recommended dosages, when taken as directed, and if the drug is misused or abused. The risk of opioid-related overdose or overdose-related death is increased with higher opioid doses, and this risk persists over the course of therapy. In postmarketing studies, addiction, abuse, misuse, and fatal and non-fatal opioid overdose were observed in patients with long-term opioid use [see Adverse Reactions (6.2)] .

Assess each patient's risk for opioid addiction, abuse, or misuse prior to prescribing ROXYBOND, and reassess all patients receiving ROXYBOND for the development of these behaviors and conditions. Risks are increased in patients with a personal or family history of substance abuse (including drug or alcohol abuse or addiction) or mental illness (e.g., major depression). The potential for these risks should not, however, prevent the proper management of pain in any given patient. Patients at increased risk may be prescribed opioids such as ROXYBOND but use in such patients necessitates intensive counseling about the risks and proper use of ROXYBOND along with frequent reevaluation for signs of addiction, abuse, and misuse. Consider recommending or prescribing an opioid overdose reversal agent [see Dosage and Administration (2.2), Warnings and Precautions (5.2), Overdosage (10)] .

Opioids are sought for nonmedical use and are subject to diversion from legitimate prescribed use. Consider these risks when prescribing or dispensing ROXYBOND. Strategies to reduce these risks include prescribing the drug in the smallest appropriate quantity and advising the patient on careful storage of the drug during the course of treatment and on the proper disposal of unused drugs. Contact local state professional licensing board or state-controlled substances authority for information on how to prevent and detect abuse or diversion of this product.

5.2 Life-Threatening Respiratory Depression

Serious, life-threatening, or fatal respiratory depression has been reported with the use of opioids, even when used as recommended. Respiratory depression, if not immediately recognized and treated, may lead to respiratory arrest and death. Management of respiratory depression may include close observation, supportive measures, and use of opioid overdose reversal agent, depending on the patient's clinical status [see Overdosage (10)] . Carbon dioxide (CO2) retention from opioid-induced respiratory depression can exacerbate the sedating effects of opioids.

While serious, life-threatening, or fatal respiratory depression can occur at any time during the use of ROXYBOND, the risk is greatest during the initiation of therapy or following a dosage increase.

To reduce the risk of respiratory depression, proper dosing and titration of ROXYBOND are essential [see Dosage and Administration (2)] . Overestimating the ROXYBOND dosage when converting patients from another opioid product can result in fatal overdose with the first dose.

Accidental ingestion of even one dose of ROXYBOND, especially by children, can result in respiratory depression and death due to an overdose of oxycodone.

Educate patients and caregivers on how to recognize respiratory depression and emphasize on the importance of calling 911 or getting emergency medical help right away in the event of a known or suspected overdose.

Opioids can cause sleep-related breathing disorders including central sleep apnea (CSA) and sleep-related hypoxemia. Opioid use increases the risk of CSA in a dose-dependent fashion. In patients who present with CSA, consider decreasing the opioid dosage using best practices for opioid taper [see Dosage and Administration (2.4, 2.5)] .

Patient Access to an Opioid Overdose Reversal Agent for the Emergency Treatment of Opioid Overdose

Inform patients and caregivers about opioid overdose reversal agents (e.g., naloxone, nalmefene). Discuss the importance of having access to an opioid overdose reversal agent, especially if the patient has risk factors for overdose (e.g., concomitant use of CNS depressants, a history of opioid use disorder, or prior opioid overdose) or if there are household members (including children) or other close contacts at risk for accidental ingestion or opioid overdose. The presence of risk factors for overdose should not prevent the management of pain in any patient [see Warnings and Precautions (5.1, 5.3)] .

Discuss the options for obtaining an opioid overdose reversal agent (e.g., prescription, over-the-counter, or as part of a community-based program).

There are important differences among the opioid overdose reversal agents, such as route of administration, product strength, approved patient age range, and pharmacokinetics. Be familiar with these differences, as outlined in the approved labeling for those products, prior to recommending or prescribing such an agent.

Educate patients and caregivers on how to recognize respiratory depression, and how to use an opioid overdose reversal agent for the emergency treatment of opioid overdose. Emphasize the importance of calling 911 or getting emergency medical help, even if an opioid overdose reversal agent is administered [see Dosage and Administration (2.2), Warnings and Precautions (5.1, 5.3), Overdosage (10)] .

5.3 Risks from Concomitant Use with Benzodiazepines or Other CNS Depressants

Profound sedation, respiratory depression, coma, and death may result from the concomitant use of ROXYBOND with benzodiazepines and/or other CNS depressants, including alcohol (e.g., non-benzodiazepine sedatives/hypnotics, anxiolytics, tranquilizers, muscle relaxants, general anesthetics, antipsychotics, gabapentinoids [gabapentin or pregabalin], and other opioids). Because of these risks, reserve concomitant prescribing of these drugs for use in patients for whom alternative treatment options are inadequate.

Observational studies have demonstrated that concomitant use of opioid analgesics and benzodiazepines increases the risk of drug-related mortality compared to use of opioid analgesics alone. Because of similar pharmacological properties, it is reasonable to expect similar risk with the concomitant use of other CNS depressant drugs with opioid analgesics [see Drug Interactions (7)] .

If the decision is made to prescribe a benzodiazepine or other CNS depressant concomitantly with an opioid analgesic, prescribe the lowest effective dosages and minimum durations of concomitant use. In patients already receiving an opioid analgesic, prescribe a lower initial dose of the benzodiazepine or other CNS depressant than indicated in the absence of an opioid, and titrate based on clinical response. If an opioid analgesic is initiated in a patient already taking a benzodiazepine or other CNS depressant, prescribe a lower initial dose of the opioid analgesic, and titrate based on clinical response. Inform patients and caregivers of this potential interaction and educate them on the signs and symptoms of respiratory depression (including sedation). If concomitant use is warranted, consider recommending or prescribing an opioid overdose reversal agent [see Dosage and Administration (2.2), Warnings and Precautions (5.2), Overdosage (10)] .

Advise both patients and caregivers about the risks of respiratory depression and sedation when ROXYBOND is used with benzodiazepines or other CNS depressants (including alcohol and illicit drugs). Advise patients not to drive or operate dangerous machinery until the effects of concomitant use of the benzodiazepine or other CNS depressant have been determined. Screen patients for risk of substance use disorders, including opioid abuse and misuse, and warn them of the risk for overdose and death associated with the use of additional CNS depressants including alcohol and illicit drugs [see Drug Interactions (7)] .

5.4 Neonatal Opioid Withdrawal Syndrome

Use of ROXYBOND for an extended period of time during pregnancy can result in withdrawal in the neonate. Neonatal opioid withdrawal syndrome, unlike opioid withdrawal syndrome in adults, may be life threatening if not recognized and treated, and requires management according to protocols developed by neonatology experts. Observe newborns for signs of neonatal opioid withdrawal syndrome and manage accordingly. Advise pregnant women using opioids for an extended period of time of the risk of neonatal opioid withdrawal syndrome and ensure that appropriate treatment will be available [see Use in Specific Populations (8.1)] .

5.5 Opioid Analgesic Risk Evaluation and Mitigation Strategy (REMS)

To ensure that the benefits of opioid analgesics outweigh the risks of addiction, abuse, and misuse, the Food and Drug Administration (FDA) has required a Risk Evaluation and Mitigation Strategy (REMS) for these products. Under the requirements of the REMS, drug companies with approved opioid analgesic products must make REMS-compliant education programs available to healthcare providers. Healthcare providers are strongly encouraged to do all of the following:

- Complete a REMS-compliant education program offered by an accredited provider of continuing education (CE) or another education program that includes all the elements of the FDA Education Blueprint for Health Care Providers Involved in the Management or Support of Patients with Pain.
- Discuss the safe use, serious risks, and proper storage and disposal of opioid analgesics with patients and/or their caregivers every time these medicines are prescribed. The Patient Counseling Guide (PCG) can be obtained at this link: www.fda.gov/OpioidAnalgesicREMSPCG.
- Emphasize to patients and their caregivers the importance of reading the Medication Guide that they will receive from their pharmacist every time an opioid analgesic is dispensed to them.
- Consider using other tools to improve patient, household, and community safety, such as patient-prescriber agreements that reinforce patient-prescriber responsibilities.

To obtain further information on the opioid analgesic REMS and for a list of accredited REMS CME/CE, call 1-800-503-0784, or log on to www.opioidanalgesicrems.com. The FDA Blueprint can be found at www.fda.gov/OpioidAnalgesicREMSBlueprint.

5.6 Risks of Concomitant Use or Discontinuation of Cytochrome P450 3A4 Inhibitors and Inducers

Concomitant use of ROXYBOND with a CYP3A4 inhibitor, such as macrolide antibiotics (e.g., erythromycin), azole-antifungal agents (e.g., ketoconazole), and protease inhibitors (e.g., ritonavir), may increase plasma concentrations of oxycodone and prolong opioid adverse reactions, which may cause potentially fatal respiratory depression [see Warnings and Precautions (5.2)] , particularly when an inhibitor is added after a stable dose of ROXYBOND is achieved. Similarly, discontinuation of a CYP3A4 inducer, such as rifampin, carbamazepine, and phenytoin, in ROXYBOND-treated patients may increase oxycodone plasma concentrations and prolong opioid adverse reactions. When using ROXYBOND with CYP3A4 inhibitors or discontinuing CYP3A4 inducers in ROXYBOND-treated patients, evaluate patients at frequent intervals and consider dosage reduction of ROXYBOND until stable drugs effects are achieved [see Drug Interactions (7)] .

Concomitant use of ROXYBOND with CYP3A4 inducers or discontinuation of a CYP3A4 inhibitor could decrease oxycodone plasma concentrations, decrease opioid efficacy or, possibly, lead to a withdrawal syndrome in a patient who had developed physical dependence to oxycodone. When using ROXYBOND with CYP3A4 inducers or discontinuing CYP3A4 inhibitors, evaluate patients at frequent intervals and consider increasing the opioid dosage if needed to maintain adequate analgesia or if symptoms of opioid withdrawal occur [see Drug Interactions (7)] .

5.7 Opioid-Induced Hyperalgesia and Allodynia

Opioid-Induced Hyperalgesia (OIH) occurs when an opioid analgesic paradoxically causes an increase in pain, or an increase in sensitivity to pain. This condition differs from tolerance, which is the need for increasing doses of opioids to maintain a defined effect [see Dependence (9.3)] . Symptoms of OIH include (but may not be limited to) increased levels of pain upon opioid dosage increase, decreased levels of pain upon opioid dosage decrease, or pain from ordinarily non-painful stimuli (allodynia). These symptoms may suggest OIH only if there is no evidence of underlying disease progression, opioid tolerance, opioid withdrawal, or addictive behavior.

Cases of OIH have been reported, both with short-term and longer-term use of opioid analgesics. Though the mechanism of OIH is not fully understood, multiple biochemical pathways have been implicated. Medical literature suggests a strong biologic plausibility between opioid analgesics and OIH and allodynia. If a patient is suspected to be experiencing OIH, carefully consider appropriately decreasing the dose of the current opioid analgesic or opioid rotation (safely switching the patient to a different opioid moiety) [ see Dosage and Administration (2.5), Warnings and Precautions (5.14) ].

5.8 Life-Threatening Respiratory Depression in Patients with Chronic Pulmonary Disease or in Elderly, Cachectic, or Debilitated Patients

The use of ROXYBOND in patients with acute or severe bronchial asthma in an unmonitored setting or in the absence of resuscitative equipment is contraindicated.

Patients with Chronic Pulmonary Disease: ROXYBOND-treated patients with significant chronic obstructive pulmonary disease or cor pulmonale, and those with a substantially decreased respiratory reserve, hypoxia, hypercapnia, or pre-existing respiratory depression are at increased risk of decreased respiratory drive including apnea, even at recommended dosages of ROXYBOND [see Warnings and Precautions (5.2)] .

Elderly, Cachectic, or Debilitated Patients: Life-threatening respiratory depression is more likely to occur in elderly, cachectic, or debilitated patients because they may have altered pharmacokinetics or altered clearance compared to younger, healthier patients [see Warnings and Precautions (5.2)] .

Regularly evaluate patients, particularly when initiating and titrating ROXYBOND and when ROXYBOND is given concomitantly with other drugs that depress respiration [see Warnings and Precautions (5.2, 5.3)] . Alternatively, consider the use of non-opioid analgesics in these patients.

5.9 Adrenal Insufficiency

Cases of adrenal insufficiency have been reported with opioid use, more often following greater than one month of use. Presentation of adrenal insufficiency may include non-specific symptoms and signs including nausea, vomiting, anorexia, fatigue, weakness, dizziness, and low blood pressure. If adrenal insufficiency is suspected, confirm the diagnosis with diagnostic testing as soon as possible. If adrenal insufficiency is diagnosed, treat with physiologic replacement doses of corticosteroids. Wean the patient off of the opioid to allow adrenal function to recover and continue corticosteroid treatment until adrenal function recovers. Other opioids may be tried as some cases reported use of a different opioid without recurrence of adrenal insufficiency. The information available does not identify any particular opioids as being more likely to be associated with adrenal insufficiency.

5.10 Severe Hypotension

ROXYBOND may cause severe hypotension including orthostatic hypotension and syncope in ambulatory patients. There is increased risk in patients whose ability to maintain blood pressure has already been compromised by a reduced blood volume or concurrent administration of certain CNS depressant drugs (e.g., phenothiazines or general anesthetics) [see Drug Interactions (7)] . Regularly evaluate these patients for signs of hypotension after initiating or titrating the dosage of ROXYBOND. In patients with circulatory shock, use of ROXYBOND may cause vasodilation that can further reduce cardiac output and blood pressure. Avoid use of ROXYBOND in patients with circulatory shock.

5.11 Risks of Use in Patients with Increased Intracranial Pressure, Brain Tumors, Head Injury, or Impaired Consciousness

In patients who may be susceptible to the intracranial effects of CO2retention (e.g., those with evidence of increased intracranial pressure or brain tumors), ROXYBOND may reduce the respiratory drive, and the resultant CO2retention can further increase intracranial pressure. Monitor such patients for signs of sedation and respiratory depression, particularly when initiating therapy with ROXYBOND.

Opioids may obscure the clinical course in a patient with a head injury. Avoid the use of ROXYBOND in patients with impaired consciousness or coma.

5.12 Risks of Gastrointestinal Complications

ROXYBOND is contraindicated in patients with known or suspected gastrointestinal obstruction, including paralytic ileus.

The oxycodone in ROXYBOND may cause spasm of the sphincter of Oddi. Opioids may cause increases in serum amylase. Regularly evaluate patients with biliary tract disease, including acute pancreatitis, for worsening symptoms.

Cases of opioid-induced esophageal dysfunction (OIED) have been reported in patients taking opioids. The risk of OIED may increase as the dose and/or duration of opioids increases. Regularly evaluate patients for signs and symptoms of OIED (e.g., dysphagia, regurgitation, non-cardiac chest pain) and, if necessary, adjust opioid therapy as clinically appropriate [see Clinical Pharmacology (12.2)] .

5.13 Increased Risk of Seizures in Patients with Seizure Disorders

The oxycodone in ROXYBOND may increase the frequency of seizures in patients with seizure disorders and may increase the risk of seizures occurring in other clinical settings associated with seizures. Regularly evaluate patients with a history of seizure disorders for worsened seizure control during ROXYBOND therapy.

5.14 Withdrawal

Do not rapidly reduce or abruptly discontinue ROXYBOND in a patient physically dependent on opioids. When discontinuing ROXYBOND in a physically-dependent patient, gradually taper the dosage. Rapid tapering of oxycodone in a patient physically dependent on opioids may lead to a withdrawal syndrome and return of pain [see Dosage and Administration (2.4, 2.5), Drug Abuse and Dependence (9.3)] .

Additionally, avoid the use of mixed agonist/antagonist (e.g., pentazocine, nalbuphine, and butorphanol) or partial agonist (e.g., buprenorphine) analgesics in patients who are receiving a full opioid agonist analgesic, including ROXYBOND. In these patients, mixed agonist/antagonist and partial agonist analgesics may reduce the analgesic effect and/or precipitate withdrawal symptoms [see Drug Interactions (7)] .

5.15 Risks of Driving and Operating Machinery

ROXYBOND may impair the mental or physical abilities needed to perform potentially hazardous activities such as driving a car or operating machinery. Warn patients not to drive or operate dangerous machinery unless they are tolerant to the effects of ROXYBOND and know how they will react to the medication.

6 ADVERSE REACTIONS

The following serious adverse reactions are described or are described in greater detail, in other sections:

- Addiction, Abuse, and Misuse [see Warnings and Precautions (5.1)]
- Life-Threatening Respiratory Depression [see Warnings and Precautions (5.2)]
- Interactions with Benzodiazepines or Other CNS Depressants [see Warnings and Precautions (5.3)]
- Neonatal Opioid Withdrawal Syndrome [see Warnings and Precautions (5.4)]
- Opioid-Induced Hyperalgesia and Allodynia [see Warnings and Precautions (5.7)]
- Adrenal Insufficiency [see Warnings and Precautions (5.9)]
- Severe Hypotension [see Warnings and Precautions (5.10)]
- Gastrointestinal Adverse Reactions [see Warnings and Precautions (5.12)]
- Seizures [see Warnings and Precautions (5.13)]
- Withdrawal [see Warnings and Precautions (5.14)]

6.1 Clinical Trials Experience

Because clinical trials are conducted under widely varying conditions, adverse reaction rates observed in the clinical trials of a drug cannot be directly compared to rates in the clinical trials of another drug and may not reflect the rates observed in practice.

Oxycodone hydrochloride tablets have been evaluated in open label clinical trials in patients with cancer and nonmalignant pain. Oxycodone hydrochloride tablets are associated with adverse experiences similar to those seen with other opioids.

Serious adverse reactions that may be associated with ROXYBOND therapy include: respiratory depression, respiratory arrest, circulatory depression, cardiac arrest, hypotension, and/or shock.

The common adverse reactions seen on initiation of therapy with oxycodone hydrochloride tablets are dose related and are opioid-related adverse reactions. The most frequent of these included nausea, constipation, vomiting, headache, pruritus, insomnia, dizziness, asthenia, and somnolence. The frequency of these reactions depended on several factors, including clinical setting, the patient's level of opioid tolerance, and host factors specific to the individual.

In all patients for whom dosing information was available (n=191) from the open-label and double-blind studies involving oxycodone hydrochloride tablets, the following adverse events were recorded in oxycodone hydrochloride treated patients with an incidence ≥ 3%. In descending order of frequency, they were: nausea, constipation, vomiting, headache, pruritus, insomnia, dizziness, asthenia, and somnolence.

Other less frequently observed adverse reactions from opioid analgesics, including oxycodone hydrochloride tablets included:

Blood and lymphatic system disorders: anemia, leukopenia

Cardiac disorders: cardiac failure, palpitation, tachycardia

Gastrointestinal disorders: abdominal pain, dry mouth, diarrhea, dyspepsia, dysphagia, glossitis, nausea, vomiting

General disorders and administration site conditions: chills, edema, edema peripheral, pain, pyrexia

Immune system disorders: hypersensitivity

Infections and infestations: bronchitis, gingivitis, infection, pharyngitis, rhinitis, sepsis, sinusitis, urinary tract infection

Injury, poisoning, and procedural complications: injury

Metabolism and nutritional disorders: decreased appetite, gout, hyperglycemia

Musculoskeletal and connective tissue disorders: arthralgia, arthritis, back pain, bone pain, myalgia, neck pain, pathological fracture

Nervous system disorders: hypertonia, hypoesthesia, migraine, neuralgia, tremor, vasodilation

Psychiatric disorders: agitation, anxiety, confusional state, nervousness, personality disorder

Respiratory, thoracic, and mediastinal disorders: cough, dyspnea, epistaxis, laryngospasm, lung disorder

Skin and subcutaneous tissue disorders: photosensitivity reaction, rash, hyperhidrosis, urticaria

Vascular disorders: thrombophlebitis, hemorrhage, hypotension, vasodilation

6.2 Postmarketing Experience

The following adverse reactions have been identified during post approval use of oxycodone. Because these reactions are reported voluntarily from a population of uncertain size, it is not always possible to reliably estimate their frequency or establish a causal relationship to drug exposure.

General disorders and administrative site disorders: drug withdrawal syndrome neonatal [see Warnings and Precautions (5.4)]

Respiratory, thoracic, and mediastinal disorders: pharyngeal edema

Serotonin syndrome: Cases of serotonin syndrome, a potentially life-threatening condition, have been reported during concomitant use of opioids with serotonergic drugs [see Drug Interactions (7)] .

Adrenal insufficiency: Cases of adrenal insufficiency have been reported with opioid use, more often following greater than one month of use [see Warnings and Precautions (5.9)] .

Anaphylaxis: Anaphylactic reaction has been reported with ingredients contained in ROXYBOND [see Contraindications (4)] .

Androgen deficiency: Cases of androgen deficiency have occurred with use of opioids for an extended period of time. [see Clinical Pharmacology (12.2)] .

Hyperalgesia and Allodynia: Cases of hyperalgesia and allodynia have been reported with opioid therapy of any duration [see Warnings and Precautions (5.7)] .

Hypoglycemia: Cases of hypoglycemia have been reported in patients taking opioids. Most reports were in patients with at least one predisposing risk factor (e.g., diabetes).

Opioid-induced esophageal dysfunction (OIED): Cases of OIED have been reported in patients taking opioids and may occur more frequently in patients taking higher doses of opioids, and/or in patients taking opioids longer term [see Warnings and Precautions (5.12)] .

Adverse Reactions from Observational Studies

A prospective, observational cohort study estimated the risks of addiction, abuse, and misuse in patients initiating long-term use of Schedule II opioid analgesics between 2017 and 2021. Study participants included in one or more analyses had been enrolled in selected insurance plans or health systems for at least one year, were free of at least one outcome at baseline, completed a minimum number of follow-up assessments, and either: 1) filled multiple extended-release/long-acting opioid analgesic prescriptions during a 90-day period (n=978); or 2) filled any Schedule II opioid analgesic prescriptions covering at least 70 of 90 days (n=1,244). Those included also had no dispensing of the qualifying opioids in the previous 6 months.

Over 12 months:

- approximately 1% to 6% of participants across the two cohorts newly met criteria for addiction, as assessed with two validated interview-based measures of moderate-to-severe opioid use disorder based on Diagnostic and Statistical Manual of Mental Disorders, Fifth Edition (DSM-5) criteria, and
- approximately 9% and 22% of participants across the two cohorts newly met criteria for prescription opioid abuse and misuse [defined in Drug Abuse and Dependence (9) ], respectively, as measured with a validated self-reported instrument.

A retrospective, observational cohort study estimated the risk of opioid-involved overdose or opioid overdose-related death in patients with new long-term use of Schedule II opioid analgesics from 2006 through 2016 (n=220,249). Included patients had been enrolled in either one of two commercial insurance programs, one managed care program, or one Medicaid program for at least 9 months. New long-term use was defined as having Schedule II opioid analgesic prescriptions covering at least 70 days' supply over the 3 months prior to study entry and none during the preceding 6 months. Patients were excluded if they had an opioid-involved overdose in the 9 months prior to study entry. Overdose was measured using a validated medical code-based algorithm with linkage to the National Death Index database. The 5-year cumulative incidence estimates for opioid-involved overdose or opioid overdose-related death ranged from approximately 1.5% to 4% across study sites, counting only the first event during follow-up. Approximately 17% of first opioid overdoses observed over the entire study period (5-11 years, depending on the study site) were fatal. Higher baseline opioid dose was the strongest and most consistent predictor of opioid-involved overdose or opioid overdose-related death. Study exclusion criteria may have selected patients at lower risk of overdose, and substantial loss to follow-up (approximately 80%) also may have biased estimates.

The risk estimates from the studies described above may not be generalizable to all patients receiving opioid analgesics, such as those with exposures shorter or longer than the duration evaluated in the studies.

7 DRUG INTERACTIONS

Table 1includes clinically significant drug interactions with ROXYBOND.

Table 1. Clinically Significant Drug Interactions with ROXYBOND
Inhibitors of CYP3A4 and CYP2D6
Clinical Impact: | The concomitant use of ROXYBOND and CYP3A4 inhibitors can increase the plasma concentration of oxycodone, resulting in increased or prolonged opioid effects. These effects could be more pronounced with concomitant use of ROXYBOND and CYP2D6 and CYP3A4 inhibitors, particularly when an inhibitor is added after a stable dose of ROXYBOND is achieved [see Warnings and Precautions (5.6)] . After stopping a CYP3A4 inhibitor, as the effects of the inhibitor decline, the oxycodone plasma concentration will decrease [see Clinical Pharmacology (12.3)] , resulting in decreased opioid efficacy or a withdrawal syndrome in patients who had developed physical dependence to oxycodone.
Intervention: | If concomitant use is necessary, consider dosage reduction of ROXYBOND until stable drug effects are achieved. Evaluate patients at frequent intervals for respiratory depression and sedation. If a CYP3A4 inhibitor is discontinued, consider increasing the ROXYBOND dosage until stable drug effects are achieved. Evaluate for signs of opioid withdrawal.
Examples: | Macrolide antibiotics (e.g., erythromycin), azole-antifungal agents (e.g., ketoconazole), protease inhibitors (e.g., ritonavir).
CYP3A4 Inducers
Clinical Impact: | The concomitant use of ROXYBOND and CYP3A4 inducers can decrease the plasma concentration of oxycodone [see Clinical Pharmacology (12.3)] , resulting in decreased efficacy or onset of a withdrawal syndrome in patients who have developed physical dependence to oxycodone [see Warnings and Precautions (5.6, 5.14)] . After stopping a CYP3A4 inducer, as the effects of the inducer decline, the oxycodone plasma concentration will increase [see Clinical Pharmacology (12.3)] , which could increase or prolong both the therapeutic effects and adverse reactions, and may cause serious respiratory depression.
Intervention | If concomitant use is necessary, consider increasing the ROXYBOND dosage until stable drug effects are achieved. Evaluate patients for signs of opioid withdrawal. If a CYP3A4 inducer is discontinued, consider ROXYBOND dosage reduction and evaluate patients at frequent intervals for signs of respiratory depression and sedation.
Examples: | Rifampin, carbamazepine, phenytoin
Benzodiazepines and Other Central Nervous System (CNS) Depressants
Clinical Impact: | Due to additive pharmacologic effect, the concomitant use of benzodiazepines or other CNS depressants, including alcohol, can increase the risk of hypotension, respiratory depression, profound sedation, coma, and death [see Warnings and Precautions (5.3)] .
Intervention: | Reserve concomitant prescribing of these drugs for use in patients for whom alternative treatment options are inadequate. Limit dosages and durations to the minimum required. Inform patients and caregivers of this potential interaction and educate them on the signs and symptoms of respiratory depression (including sedation). If concomitant use is warranted, consider recommending or prescribing an opioid overdose reversal agent [see Dosage and Administration (2.2), Warnings and Precautions (5.1, 5.2, 5.3)].
Examples: | Benzodiazepines and other sedatives/hypnotics, anxiolytics, tranquilizers, muscle relaxants, general anesthetics, antipsychotics, gabapentinoids (gabapentin or pregabalin), other opioids, alcohol.
Serotonergic Drugs
Clinical Impact: | The concomitant use of opioids with other drugs that affect the serotonergic neurotransmitter system has resulted in serotonin syndrome [see Adverse Reactions (6.2)] .
Intervention: | If concomitant use is warranted, frequently reevaluate the patient, particularly during treatment initiation and dose adjustment. Discontinue ROXYBOND if serotonin syndrome is suspected.
Examples: | Selective serotonin reuptake inhibitors (SSRIs), serotonin and norepinephrine reuptake inhibitors (SNRIs), tricyclic antidepressants (TCAs), triptans, 5-HT3 receptor antagonists, drugs that affect the serotonin neurotransmitter system (e.g., mirtazapine, trazodone, tramadol), certain muscle relaxants (i.e., cyclobenzaprine, metaxalone), monoamine oxidase inhibitors (those intended to treat psychiatric disorders and also others, such as linezolid and intravenous methylene blue).
Monoamine Oxidase Inhibitors (MAOIs)
Clinical Impact: | MAOI interactions with opioids may manifest as serotonin syndrome or opioid toxicity (e.g., respiratory depression, coma) [see Warnings and Precautions (5.2)] .
Intervention: | The use of ROXYBOND is not recommended for patients taking MAOIs or within 14 days of stopping such treatment. If urgent use of an opioid is necessary, use test doses and frequent titration of small doses to treat pain while closely monitoring blood pressure and signs and symptoms of CNS and respiratory depression.
Examples: | Phenelzine, tranylcypromine, linezolid
Mixed Agonist/Antagonist Opioid Analgesics
Clinical Impact: | May reduce the analgesic effect of ROXYBOND and/or may precipitate withdrawal symptoms.
Intervention: | Avoid concomitant use
Examples: | Butorphanol, nalbuphine, pentazocine, buprenorphine
Muscle Relaxants
Clinical Impact: | Oxycodone may enhance the neuromuscular blocking action of skeletal muscle relaxants and produce an increased degree of respiratory depression.
Intervention: | Because respiratory depression may be greater than otherwise expected, decrease the dosage of ROXYBOND and/or the muscle relaxant as necessary. Due to the risk of respiratory depression with concomitant use of skeletal muscle relaxants and opioids, consider recommending or prescribing an opioid overdose reversal agent [see Dosage and Administration (2.2), Warnings and Precautions (5.2, 5.3)] .
Examples: | Cyclobenzaprine, metaxalone
Diuretics
Clinical Impact: | Opioids can reduce the efficacy of diuretics by inducing the release of antidiuretic hormone.
Intervention: | Evaluate patients for signs of diminished diuresis and/or effects on blood pressure and increase the dosage of the diuretic as needed.
Anticholinergic Drugs
Clinical Impact: | The concomitant risk of anticholinergic drugs may result in increased risk of urinary retention and/or severe constipation, which may lead to paralytic ileus.
Intervention: | Evaluate patients for signs of urinary retention or reduced gastric motility when ROXYBOND is used concurrently with anticholinergic drugs.

8 USE IN SPECIFIC POPULATIONS

8.1 Pregnancy

Risk Summary

Use of opioid analgesics for an extended period of time during pregnancy may cause neonatal opioid withdrawal syndrome [see Warnings and Precautions (5.4), Clinical Considerations)] . There are reports of respiratory depression when oxycodone is used during labor and delivery [see Clinical Considerations] . There are no available data with ROXYBOND in pregnant women to inform a drug-associated risk for adverse developmental outcomes. Animal reproduction studies with oral administrations of oxycodone hydrochloride in rats and rabbits during the period of organogenesis, at doses 2.6 and 8.1 times, respectively, the human dose of 60 mg/day did not reveal evidence of teratogenicity or embryo-fetal toxicity. In several published studies, treatment of pregnant rats with oxycodone at clinically relevant doses and below, resulted in neurobehavioral effects in offspring [see Data)] . Based on animal data, advise pregnant women of the potential risk to a fetus.

The risk of major birth defects and miscarriage for the indicated population is unknown. All pregnancies have a background risk of birth defects, loss, or other adverse outcomes. In the U.S. general population, the estimated background risk of major birth defects and miscarriage in clinically recognized pregnancies is 2% to 4% and 15% to 20%, respectively.

Clinical Considerations

Fetal/Neonatal Adverse Reactions

Use of opioid analgesics for an extended period of time during pregnancy for medical or nonmedical purposes can result in physical dependence in the neonate and neonatal opioid withdrawal syndrome shortly after birth.

Neonatal opioid withdrawal syndrome presents as irritability, hyperactivity, and abnormal sleep pattern, high pitched cry, tremor, vomiting, diarrhea, and failure to gain weight. The onset, duration, and severity of neonatal opioid withdrawal syndrome vary based on the specific opioid used, duration of use, timing and amount of last maternal use, and rate of elimination of the drug by the newborn. Observe newborns for symptoms of neonatal opioid withdrawal syndrome and manage accordingly [see Warnings and Precautions (5.4)] .

Labor or Delivery

Opioids cross the placenta and may produce respiratory depression and psycho-physiologic effects in neonates. An opioid overdose reversal agent, such as naloxone or nalmefene, must be available for reversal of opioid-induced respiratory depression in the neonate. ROXYBOND is not recommended for use in pregnant women during or immediately prior to labor, when other analgesic techniques are more appropriate. Opioid analgesics, including ROXYBOND, can prolong labor through actions which temporarily reduce the strength, duration, and frequency of uterine contractions. However, this effect is not consistent and may be offset by an increased rate of cervical dilation, which tends to shorten labor. Monitor neonates exposed to opioid analgesics during labor for signs of excess sedation and respiratory depression.

Data

Human Data

Limited published data from case-control and observational studies on oxycodone use during pregnancy are inconsistent in their findings. Although some studies reported an increased risk of congenital malformations, there was no consistent pattern of malformations noted. In addition, multiple similar studies reported no association. Methodological limitations of these studies, including small sample size, recall bias, lack of information regarding dose and timing of exposure and concomitant use of other medications, preclude a reliable evaluation of the potential risk of adverse fetal outcomes with the use of oxycodone in pregnancy.

Animal Data

In embryo-fetal development studies in rats and rabbits, pregnant animals received oral doses of oxycodone hydrochloride administered during the period of organogenesis up to 16 mg/kg/day and up to 25 mg/kg/day, respectively. These studies revealed no evidence of teratogenicity or embryo fetal toxicity due to oxycodone. The highest doses tested in rats and rabbits were equivalent to approximately 2.6 and 8.1 times an adult human dose of 60 mg/day, respectively, on a mg/m^2basis. In published studies, offspring of pregnant rats administered oxycodone during gestation have been reported to exhibit neurobehavioral effects including altered stress responses, increased anxiety-like behavior (2 mg/kg/day IV from Gestation Day 8 to 21 and Postnatal Day 1, 3, and 5; 0.3-times an adult human dose of 60 mg/day, on a mg/m^2basis) and altered learning and memory (15 mg/kg/day orally from breeding through parturition; 2.4 times an adult human dose of 60 mg/day, on a mg/m^2basis).

8.2 Lactation

Risk Summary

Available data from lactation studies indicate that oxycodone is present in breastmilk and that doses of less than 60 mg/day of the immediate-release formulation are unlikely to result in clinically relevant exposures in breastfed infants. A pharmacokinetics study utilizing opportunistic sampling of 76 lactating women receiving oxycodone immediate-release products for postpartum pain management showed that oxycodone concentrates in breastmilk with an average milk to plasma ratio of 3.2. The relative infant dose was low, approximately 1.3% of a weight-adjusted maternal dose [see Data)] .

In the same study, among the 70 infants exposed to oxycodone in breastmilk, no adverse events were attributed to oxycodone. However, based on known adverse effects in adults, infants should be monitored for signs of excess sedation and respiratory depression [see Clinical Considerations)] . There are no data on the effects of the oxycodone on milk production.

The developmental and health benefits of breastfeeding should be considered along with the mother's clinical need for ROXYBOND and any potential adverse effects on the breastfed infant from ROXYBOND or from the underlying maternal condition.

Clinical Considerations

Monitor infants exposed to ROXYBOND through breast milk for excess sedation and respiratory depression. Withdrawal symptoms can occur in breastfed infants when maternal administration of an opioid analgesic is stopped or when breast-feeding is stopped.

Data

Oxycodone concentration data from 76 lactating women receiving immediate-release oxycodone products for postpartum pain management, and 28 infants exposed to oxycodone in breastmilk showed that following a median (range) dose of oxycodone in mothers of 9.2 (5-10) mg/dose or 33.0 (5.4-59.3) mg/day, oxycodone concentrated in breastmilk with a median (range) milk to plasma ratio of 3.2 (1.2-5.3). However, when using maternal breastmilk data to estimate the daily and relative infant dose, the infant dose was 0.006 mg/kg/day, which is 1.3% of a weight-adjusted maternal dose of 10 mg every 6 hours. These estimates based on maternal breastmilk concentrations were corroborated by the observed infant concentrations, of which over 75% (19/25) were below the limit of quantification. Among the 6 infants with quantifiable concentration, the median (range) concentration was 0.2 ng/mL (0.1-0.7). These concentrations are 100 to 1000 times lower than concentrations observed in other studies after infants received oxycodone at 0.1 mg/kg/dose (~20-200 ng/mL).

8.3 Females and Males of Reproductive Potential

Infertility

Use of opioids for an extended period of time may cause reduced fertility in females and males of reproductive potential. It is not known whether these effects on fertility are reversible [see Clinical Pharmacology (12.2), and Nonclinical Toxicology (13.1)] .

8.4 Pediatric Use

The safety and efficacy of ROXYBOND in pediatric patients have not been evaluated.

8.5 Geriatric Use

Of the total number of subjects in clinical studies of oxycodone hydrochloride, 20.8% (112/538) were 65 and over, while 7.2% (39/538) were 75 and over. No overall differences in safety or effectiveness were observed between these subjects and younger subjects, and other reported clinical experience has not identified differences in responses between the elderly and younger patients, but greater sensitivity of some older individuals cannot be ruled out.

Elderly patients (aged 65 years or older) may have increased sensitivity to oxycodone. In general, use caution when selecting a dosage for an elderly patient, usually starting at the low end of the dosing range, reflecting the greater frequency of decreased hepatic, renal, or cardiac function and of concomitant disease or other drug therapy.

Respiratory depression is the chief risk for elderly patients treated with opioids and has occurred after large initial doses were administered to patients who were not opioid-tolerant or when opioids were co-administered with other agents that depress respiration. Titrate the dosage of ROXYBOND slowly in geriatric patients and frequently reevaluate the patient for signs of central nervous system and respiratory depression [see Warnings and Precautions (5.8)] .

Oxycodone is known to be substantially excreted by the kidney, and the risk of adverse reactions to this drug may be greater in patients with impaired renal function. Because elderly patients are more likely to have decreased renal function, care should be taken in dose selection, and it may be useful to regularly evaluate renal function.

8.6 Hepatic Impairment

Because oxycodone is extensively metabolized in the liver, its clearance may decrease in patients with hepatic impairment. Initiate therapy in these patients with a lower than usual dosage of ROXYBOND and titrate carefully. Regularly evaluate for adverse events such as respiratory depression, sedation, and hypotension [see Clinical Pharmacology (12.3)] .

8.7 Renal Impairment

Because oxycodone is known to be substantially excreted by the kidney, its clearance may decrease in patients with renal impairment. Initiate therapy with a lower than usual dosage of ROXYBOND and titrate carefully. Regularly evaluate for adverse events such as respiratory depression, sedation, and hypotension [see Clinical Pharmacology (12.3)] .

9 DRUG ABUSE AND DEPENDENCE

9.1 Controlled Substance

ROXYBOND contains oxycodone, a Schedule II controlled substance.

9.2 Abuse

ROXYBOND contains oxycodone, a substance with high potential for misuse and abuse, which can lead to the development of substance use disorder, including addiction [see Warnings and Precautions (5.1)] .

Misuse is the intentional use, for therapeutic purposes, of a drug by an individual in a way other than prescribed by a healthcare provider or for whom it was not prescribed.

Abuse is the intentional, non-therapeutic use of a drug, even once, for its desirable psychological or physiological effects.

Drug addiction is a cluster of behavioral, cognitive, and physiological phenomena that may include a strong desire to take the drug, difficulties in controlling drug use (e.g., continuing drug use despite harmful consequences, giving a higher priority to drug use than other activities and obligations), and possible tolerance or physical dependence.

Misuse and abuse of ROXYBOND increases risk of overdose, which may lead to central nervous system and respiratory depression, hypotension, seizures, and death. The risk is increased with concurrent abuse of ROXYBOND with alcohol and/or other CNS depressants. Abuse of and addiction to opioids in some individuals may not be accompanied by concurrent tolerance and symptoms of physical dependence. In addition, abuse of opioids can occur in the absence of addiction.

All patients treated with opioids require careful and frequent reevaluation for signs of misuse, abuse, and addiction, because use of opioid analgesic products carries the risk of addiction even under appropriate medical use. Patients at high risk of ROXYBOND abuse include those with a history of prolonged use of any opioid, including products containing oxycodone, those with a history of drug or alcohol abuse, or those who use ROXYBOND in combination with other abused drugs.

“Drug-seeking” behavior is very common in persons with substance use disorders. Drug-seeking tactics include emergency calls or visits near the end of office hours, refusal to undergo appropriate examination, testing, or referral, repeated “loss” of prescriptions, tampering with prescriptions, and reluctance to provide prior medical records or contact information for other treating healthcare provider(s). “Doctor shopping” (visiting multiple prescribers to obtain additional prescriptions) is common among people who abuse drugs and people with substance use disorder. Preoccupation with achieving adequate pain relief can be appropriate behavior in a patient with inadequate pain control.

ROXYBOND, like other opioids, can be diverted for nonmedical use into illicit channels of distribution. Careful record-keeping of prescribing information, including quantity, frequency, and renewal requests, as required by state and federal law, is strongly advised.

Proper assessment of the patient, proper prescribing practices, periodic reevaluation of therapy, and proper dispensing and storage are appropriate measures that help to limit abuse of opioid drugs.

Risks Specific to Abuse of ROXYBOND

Abuse of ROXYBOND poses a risk of overdose and death. This risk is increased with concurrent use of ROXYBOND with alcohol and/or other CNS depressants.

ROXYBOND is for oral use only.

Parenteral abuse of ROXYBOND can be expected to result in local tissue necrosis, infection, pulmonary granulomas, and increased risk of endocarditis and valvular heart injury. Injection of excipients included in the ROXYBOND formulation, intended to provide abuse-deterrent properties, may be associated with additional unknown serious risks. Parenteral drug abuse is commonly associated with transmission of infectious diseases such as hepatitis and HIV.

Abuse Deterrence Studies

ROXYBOND is formulated with inactive ingredients that make the tablet more difficult to manipulate for misuse and abuse even if the tablet is subjected to physical manipulation and/or chemical extraction. To evaluate the ability of the abuse-deterrent technology to reduce the potential for abuse of ROXYBOND, a series of in vitro laboratory manipulation, extraction, and syringe ability studies were conducted. An in vivo intranasal clinical abuse potential study was also conducted.

In Vitro Testing

ROXYBOND has been tested in vitro using methods of manipulation that drug abusers commonly use for preparation of opioids for administration by various routes, including oral consumption, intranasal insufflation, and injection.

Abusers may manipulate prescription opioids in order to prepare the tablets for oral, intranasal, or intravenous administration. The laboratory test data demonstrated that, relative to oxycodone immediate-release tablets, ROXYBOND has increased resistance to cutting, crushing, grinding, or breaking using selected tools. In addition, the intact and manipulated tablets resisted extraction in selected household and laboratory solvents under various conditions, including selected pre-treatments. Relative to oxycodone immediate-release tablets, the formulation forms a viscous material that resists passage through a needle; it was also more difficult to prepare solutions suitable for intravenous injection.

Clinical Abuse Potential Studies

A randomized, double-blind, double-dummy, placebo-controlled, single-dose four-way crossover study in 29 non-dependent recreational opioid users with a history of intranasal drug abuse was performed to determine the relative bioavailability and abuse potential of crushed intranasal ROXYBOND 30 mg tablets compared with crushed intranasal 30 mg oxycodone immediate-release tablets and intact orally administered ROXYBOND 30 mg tablets. Intact oral ROXYBOND tablets were included as a reference for evaluating abuse potential after manipulation and administration via an unintended route.

Drug liking was measured on a 100-mm bipolar visual analog scale (VAS) where 50 represents a neutral response of neither liking nor disliking, 0 represents maximum disliking, and 100 represents maximum liking. Response to whether the subject would be willing to take the study drug again was also measured on a bipolar 0 to 100 VAS where 50 represents a neutral response, 0 represents the strongest negative response (“definitely would not take drug again”) and 100 represents the strongest positive response (“definitely would take drug again”).

The pharmacokinetic profiles of oxycodone were also determined in this study (Table 2). When crushed and insufflated, ROXYBOND showed a lower peak oxycodone plasma concentration (Cmax~28% reduction) and a 35% longer time to peak plasma concentration (Tmax) relative to crushed and insufflated oxycodone immediate-release tablets. Similar results were demonstrated when crushed and insufflated ROXYBOND was compared to intact oral ROXYBOND with a reduction in Cmaxand a longer time to Tmax. Intact oral ROXYBOND resulted in a Cmaxof oxycodone similar to that of crushed and insufflated oxycodone immediate-release tablets, with a similar Tmax.

Table 2 Summary of Plasma Oxycodone Pharmacokinetic Parameters From the Intranasal Abuse Potential Study (n=31)
Treatment or Comparison | Cmax (ng/mL) LS Mean | AUC 0-t (ng*hr/mL) LS Mean | Tmax (hr) Median
Crushed, Insufflated oxycodone immediate-release tablets 30 mg | 55.56 | 330.77 | 1.7
Crushed, Insufflated ROXYBOND 30 mg | 40.04 | 309.21 | 2.3
Intact, oral ROXYBOND | 56.97 | 265.38 | 1.3
AUC 0-t= Area under the plasma concentration vs time curve from 0 to last measurable concentration.

Compared to crushed intranasal oxycodone immediate-release tablets, intranasal administration of crushed ROXYBOND was associated with statistically significantly lower drug liking (Emax) and take drug again (Emax) scores, as summarized in Table 3. Similar reductions in drug liking and willingness to take the drug again were reported for crushed intranasal ROXYBOND relative to intact oral ROXYBOND. These data are consistent with the slowing of the intended immediate-release properties of ROXYBOND when manipulated then insufflated compared to taking ROXYBOND orally intact. No statistically significant differences in Emaxof Drug Liking or Take Drug Again were observed between crushed intranasal oxycodone immediate-release tablets and intact oral ROXYBOND.

Table 3. Summary of Maximum Drug Liking (Emax), and Take Drug Again (Emax), Following Administration of ROXYBOND, Oxycodone Immediate-release Tablets, and Placebo in Recreational Opioid Users (N=29)
VAS |  | Crushed Intranasal ROXYBOND 30 mg | Crushed Intranasal Oxycodone immediate- release tablets 30 mg | Intact Oral ROXYBOND 30 mg | Placebo
Drug Liking (Emax) | Mean (SD) | 71.1 (12.01) | 82.9 (11.55) | 81.5 (11.49) | 53.4 (6.34)
 | Median (Range) | 71 (50 to 100) | 82 (50 to 100) | 82.00 (56 to 100) | 51.0 (50 to 77)
Take Drug Again (Emax) | Mean (SD) | 62.2 (24.51) | 82.1 (16.44) | 77.3 (18.11) | 41.9 (20.09)
 | Median (Range) | 62.0 (3 to 99) | 86.0 (37 to 100) | 81.0 (13 to 100) | 50.0 (0.0 to 78)

Figure 1. Mean Drug Liking VAS Scores Over Time (N=29)

The majority of subjects (86%; n=25) experienced some reduction in Emaxof Drug Liking VAS with crushed intranasal ROXYBOND compared with crushed intranasal oxycodone immediate-release tablets, whereas 59% (n=17) experienced at least a 30% reduction in Emaxof drug liking and 21% (n=6) experienced at least a 50% reduction in Emaxof drug liking.

Summary

The in vitro data demonstrate that ROXYBOND has physicochemical properties expected to make abuse via injection difficult. The data from the clinical study, along with support from in vitro data, also indicate that ROXYBOND has physicochemical properties that are expected to reduce abuse by the intranasal route of administration. However, abuse by the intranasal, oral, and intravenous route is still possible.

Additional data, including epidemiological data, when available, may provide further information on the impact of the current formulation of ROXYBOND on the abuse liability of the drug. Accordingly, this section may be updated in the future as appropriate.

9.3 Dependence

Both tolerance and physical dependence can develop during use of opioid therapy.

Tolerance is a physiological state characterized by a reduced response to a drug after repeated administration (i.e., a higher dose of a drug is required to produce the same effect that was once obtained at a lower dose).

Physical dependence is a state that develops as a result of a physiological adaptation in response to repeated drug use, manifested by withdrawal signs and symptoms after abrupt discontinuation or a significant dose reduction of a drug.

Withdrawal may be precipitated through the administration of drugs with opioid antagonist activity (e.g., naloxone, nalmefene), mixed agonist/antagonist analgesics (e.g., pentazocine, butorphanol, nalbuphine), or partial agonists (e.g., buprenorphine). Physical dependence may not occur to a clinically significant degree until after several days to weeks of continued use.

Do not rapidly reduce or abruptly discontinue ROXYBOND in a patient physically dependent on opioids. Rapid tapering of ROXYBOND in a patient physically dependent on opioids may lead to serious withdrawal symptoms, uncontrolled pain, and suicide. Rapid discontinuation has also been associated with attempts to find other sources of opioid analgesics, which may be confused with drug-seeking for abuse.

When discontinuing ROXYBOND, gradually taper the dosage using a patient-specific plan that considers the following: the dose of ROXYBOND the patient has been taking, the duration of treatment, and the physical and psychological attributes of the patient. To improve the likelihood of a successful taper and minimize withdrawal symptoms, it is important that the opioid tapering schedule is agreed upon by the patient. In patients taking opioids for an extended period of time at high doses, ensure that a multimodal approach to pain management, including mental health support (if needed), is in place prior to initiating an opioid analgesic taper [see Dosage and Administration (2.4, 2.5), and Warnings and Precautions (5.14)] .

Infants born to mothers physically dependent on opioids will also be physically dependent and may exhibit respiratory difficulties and withdrawal signs [see Warnings and Precautions (5.4), Use in Specific Populations (8.1)] .

10 OVERDOSAGE

Clinical Presentation

Acute overdose with oxycodone can be manifested by respiratory depression, somnolence progressing to stupor or coma, skeletal muscle flaccidity, cold and clammy skin, constricted pupils, and, in some cases, pulmonary edema, bradycardia, hypotension, hypoglycemia, partial or complete airway obstruction, atypical snoring, and death. Marked mydriasis rather than miosis may be seen with hypoxia in overdose situations [see Clinical Pharmacology (12.2)] . Toxic leukoencephalopathy has been reported after opioid overdose and can present hours, days, or weeks after apparent recovery from the initial intoxication.

Treatment of Overdose

In case of overdose, priorities are the re-establishment of a patent and protected airway and institution of assisted or controlled ventilation, if needed. Employ other supportive measures (including oxygen and vasopressors) in the management of circulatory shock and pulmonary edema as indicated. Cardiac arrest or arrhythmias will require advance life-support measures.

For clinically significant respiratory or circulatory depression secondary to oxycodone overdose, administer an opioid overdose reversal agent such as naloxone or nalmefene.

Because the duration of opioid reversal is expected to be less than the duration of action of oxycodone in ROXYBOND, carefully monitor the patient until spontaneous respiration is reliably reestablished. If the response to an opioid overdose reversal agent is suboptimal or only brief in nature, administer additional reversal agent as directed by the product's prescribing information.

In an individual physically dependent on opioids, administration of the recommended usual dosage of the opioid overdose reversal agent will precipitate an acute withdrawal syndrome. The severity of the withdrawal symptoms experienced will depend on the degree of physical dependence and the dose of the reversal agent administered. If a decision is made to treat serious respiratory depression in the physically dependent patient, administration of the reversal agent should be initiated with care and by titration with smaller than usual doses of the reversal agent.

11 DESCRIPTION

ROXYBOND (oxycodone hydrochloride) tablets for oral administration are available in 5 mg, 10 mg, 15 mg, and 30 mg strengths, each containing an equivalent of 4.5 mg, 9.0 mg, 13.5 mg, and 27 mg of oxycodone free base, respectively.

Oxycodone hydrochloride is an opioid agonist. It is a white, odorless crystalline powder derived from the opium alkaloid, thebaine. Oxycodone hydrochloride dissolves in water (1 g in 6 to 7 mL) and is considered slightly soluble in alcohol (octanol water partition coefficient is 0.7).

Chemically, oxycodone hydrochloride is 4, 5α-epoxy-14-hydroxy-3-methoxy-17-methylmorphinan-6-one hydrochloride and has the following structural formula:

Each ROXYBOND tablet contains the following inactive ingredients common to all strengths: alginic acid, ammonium hydroxide, colloidal silicon dioxide, dibutyl sebacate, dimethylaminoethyl methacrylate copolymer, ethyl acrylate and methyl methacrylate copolymer dispersion, ethylcellulose, hypromellose, iron oxide black, isopropyl alcohol, lactose monohydrate, magnesium stearate, mannitol, microcrystalline cellulose, n-butyl alcohol, polyethylene glycol, polysorbate 80, polyvinyl alcohol, propylene glycol, shellac in ethanol, sodium alginate, talc, titanium dioxide, and xanthan gum.

The 10 mg ROXYBOND tablets also contain: FD&C Red No. 40, D&C Red No. 30, and D&C Yellow No. 10.

The 15 mg ROXYBOND tablets also contain: FD&C Blue No. 2 and iron oxide yellow.

The 30 mg ROXYBOND tablets also contain: FD&C Blue No. 2.

12 CLINICAL PHARMACOLOGY

12.1 Mechanism of Action

Oxycodone is a full opioid agonist and is relatively selective for the mu-opioid receptor, although it can bind to other opioid receptors at higher doses. The principal therapeutic action of oxycodone is analgesia. Like all full opioid agonists, there is no ceiling effect for analgesia with oxycodone. Clinically, dosage is titrated to provide adequate analgesia and may be limited by adverse reactions, including respiratory and CNS depression.

The precise mechanism of the analgesic action is unknown. However, specific CNS opioid receptors for endogenous compounds with opioid-like activity have been identified throughout the brain and spinal cord and are thought to play a role in the analgesic effects of this drug.

12.2 Pharmacodynamics

Effects on the Central Nervous System

Oxycodone produces respiratory depression by direct action on brain stem respiratory centers. The respiratory depression involves a reduction in the responsiveness of the brain stem respiratory centers to both increases in carbon dioxide tension and electrical stimulation.

Oxycodone causes miosis, even in total darkness. Pinpoint pupils are a sign of opioid overdose but are not pathognomonic (e.g., pontine lesions of hemorrhagic or ischemic origins may produce similar findings). Marked mydriasis rather than miosis may be seen due to hypoxia in overdose situations.

Effects on Gastrointestinal Tract and Other Smooth Muscle

Oxycodone causes a reduction in motility associated with an increase in smooth muscle tone in the antrum, stomach, and duodenum. Digestion of food in the small intestine is delayed and propulsive contractions are decreased. Propulsive peristaltic waves in the colon are decreased, while tone may be increased to the point of spasm, resulting in constipation. Other opioid-induced effects may include a reduction in biliary and pancreatic secretions, spasm of sphincter of Oddi, transient elevations in serum amylase, and opioid-induced esophageal dysfunction (OIED).

Effects on Cardiovascular System

Oxycodone produces peripheral vasodilatation, which may result in orthostatic hypotension or syncope. Manifestations of histamine release and/or peripheral vasodilatation may include pruritus, flushing, red eyes, sweating, and/or orthostatic hypotension.

Effects on the Endocrine System

Opioids inhibit the secretion of adrenocorticotropic hormone (ACTH), cortisol, and luteinizing hormone (LH) in humans [see Adverse Reactions (6.2)] . They also stimulate prolactin, growth hormone (GH) secretion, and pancreatic secretion of insulin and glucagon.

Use of opioids for an extended period of time may influence the hypothalamic-pituitary-gonadal axis, leading to androgen deficiency that may manifest as low libido, impotence, erectile dysfunction, amenorrhea, or infertility. The causal role of opioids in the clinical syndrome of hypogonadism is unknown because the various medical, physical, lifestyle, and psychological stressors that may influence gonadal hormone levels have not been adequately controlled for in studies conducted to date [see Adverse Reactions (6.2)] .

Effects on the Immune System

Opioids have been shown to have a variety of effects on components of the immune system in in vitro and animal models. The clinical significance of these findings is unknown. Overall, the effects of opioids appear to be modestly immunosuppressive.

Concentration–Efficacy Relationships

The minimum effective analgesic concentration will vary widely among patients, especially among patients who have been previously treated with opioid agonists. The minimum effective analgesic concentration of oxycodone for any individual patient may increase over time due to an increase in pain, the development of a new pain syndrome, and/or the development of analgesic tolerance [see Dosage and Administration (2.1, 2.4), Warnings and Precautions (5.7)] .

Concentration–Adverse Reaction Relationships

There is a relationship between increasing oxycodone plasma concentration and increasing frequency of dose-related opioid adverse reactions such as nausea, vomiting, CNS effects, and respiratory depression. In opioid-tolerant patients, the situation may be altered by the development of tolerance to opioid-related adverse reactions [see Dosage and Administration (2.1, 2.2, 2.3), Warnings and Precautions (5.7)] .

12.3 Pharmacokinetics

The activity of ROXYBOND tablets is primarily due to the parent drug oxycodone. ROXYBOND tablets are designed to provide immediate-release of oxycodone.

Oxycodone pharmacokinetics are similar for ROXYBOND and oxycodone immediate-release tablets. In the fasted state, the extent of absorption (AUC) is equivalent, the rate of absorption (Cmax) is similar, and median Tmaxis slightly longer (1.0 to 1.8 h).

Table 4. Pharmacokinetic Parameters (Mean ± SD)
Dose\Parameters | AUC 0-t (ng∙hr/mL) | AUC 0-inf (ng∙hr/mL) | Cmax (ng/mL) | Tmax (hr) | Half Life (hr)
Single Dose Pharmacokinetics Study
ROXYBOND 5 mg tab (fasted) | 45.5±15.4 | 49.0±16.1 | 8.3±2.1 | 1.5a (0.7 to 5.0) | 3.9±1.2
ROXYBOND 15 mg tab (fasted) | 127.5±38.1 | 131.6±39.0 | 22.0±5.8 | 1.7a (1.0 to 12.0) | 4.1±0.8
ROXYBOND 30 mg tab (fasted) | 277.0±89.6 | 285.8±94.1 | 48.5±15.9 | 1.5a (1.0 to 8.0) | 4.3±1.0
Single Dose Food-Effect Study
ROXYBOND 30 mg tab (fasted) | 287.4±65.8 | 292.7±67.4 | 57.8±18.0 | 1.8a (0.8 to 5.0) | 3.8±0.7
ROXYBOND 30 mg tab (fed) | 354.2±82.5 | 361.9±86.7 | 68.0±20.1 | 2.0a (1.0 to 6.1) | 3.9±0.6
aMedian (range)

Absorption

About 60% to 87% of an oral dose of oxycodone reaches the systemic circulation in comparison to a parenteral dose. This high oral bioavailability (compared to other oral opioids) is due to lower presystemic and/or first-pass metabolism of oxycodone. Dose proportionality of oxycodone has been established using the ROXYBOND 5 mg, 15 mg, and 30 mg tablets based on maximum plasma concentration (Cmax) and extent of absorption (AUC) (Figure 2). It takes approximately 18 to 24 hours to reach steady-state plasma concentrations of oxycodone with oxycodone hydrochloride.

Figure 2. Mean Oxycodone Pharmacokinetic Profiles of 5-, 15-, 30-mg ROXYBOND Tablets (n=51)

Food Effect

A single-dose food effect study was conducted in normal volunteers using the 30-mg tablet. The concurrent intake of a high fat meal was shown to enhance the extent (23% increase in AUC), and the rate (18% increase in Cmax) of oxycodone absorption from the 30-mg tablet (Table 4). In addition, food caused a slight delay in Tmax(1.8 to 2 hours). Similar effects of food are expected with the 5-mg and 15-mg tablets.

Distribution

Following intravenous administration, the volume of distribution (Vss) for oxycodone was 2.6 L/kg. Plasma protein binding of oxycodone at 37°C and a pH of 7.4 was about 45%. Oxycodone has been found in breast milk [see Use in Specific Populations (8.2)] .

Elimination

Metabolism

A high proportion of oxycodone is N-dealkylated to noroxycodone during first-pass metabolism, and is catalyzed by CYP3A4. Oxymorphone is formed by the O-demethylation of oxycodone. The metabolism of oxycodone to oxymorphone is catalyzed by CYP2D6 [see Drug Interactions (7)] . Free and conjugated noroxycodone, free and conjugated oxycodone, and oxymorphone are excreted in human urine following a single oral dose of oxycodone. The major circulating metabolite is noroxycodone with an AUC ratio of 0.6 relative to that of oxycodone. Oxymorphone is present in the plasma only in low concentrations. The analgesic activity profile of other metabolites is not known at present.

Excretion

Oxycodone and its metabolites are excreted primarily via the kidney. The amounts measured in the urine have been reported as follows: free oxycodone up to 19%; conjugated oxycodone up to 50%; free oxymorphone 0%; conjugated oxymorphone ≤ 14%; both free and conjugated noroxycodone have been found in the urine but not quantified. The total plasma clearance was 0.8 L/min for adults. Apparent elimination half-life of oxycodone following the administration of ROXYBOND was 3.8 to 4.3 hours.

Specific Populations

Age: Geriatric Patients

Population pharmacokinetic studies conducted with oxycodone hydrochloride, indicated that the plasma concentrations of oxycodone did not appear to be increased in patients over the age of 65 [see Use in Specific Populations (8.5)] .

Hepatic Impairment

In a clinical trial supporting the development of oxycodone hydrochloride tablets, too few patients with decreased hepatic function were evaluated to study these potential differences. However, because oxycodone is extensively metabolized in the liver, its clearance may decrease in hepatic impaired patients [see Use in Specific Populations (8.6)] .

Renal Impairment

This drug is known to be substantially excreted by the kidney, and the risk of adverse reactions to this drug may be greater in patients with impaired renal function [see Use in Specific Populations (8.7)] .

13 NONCLINICAL TOXICOLOGY

13.1 Carcinogenesis, Mutagenesis, Impairment of Fertility

Carcinogenesis

Long-term studies have not been performed in animals to evaluate the carcinogenic potential of oxycodone.

Mutagenesis

Oxycodone hydrochloride was genotoxic in an in vitro mouse lymphoma assay in the presence of metabolic activation. There was no evidence of genotoxic potential in an in vitro bacterial reverse mutation assay (Salmonella typhimurium and Escherichia coli) or in an assay for chromosomal aberrations (in vivomouse bone marrow micronucleus assay).

Impairment of Fertility

Studies in animals to evaluate the potential impact of oxycodone on fertility have not been conducted.

16 HOW SUPPLIED/STORAGE AND HANDLING

ROXYBOND (oxycodone hydrochloride) tablets are supplied as 5 mg, 10 mg, 15 mg, and 30 mg strength round and color coated tablets with ink-prints on one side. The tablets are packaged in 100 tablet opaque HDPE bottles.

NDC | Strength | Tablet Shape | Tablet Color | Ink-Print on Tablet Side 1 | Ink-Print on Tablet Side 2
81140-101-10 | 5 mg | Round coated tablets | White | IDT/O 5 | None
81140-104-10 | 10 mg | Round coated tablets | Pink | IDT/O 10 | None
81140-102-10 | 15 mg | Round coated tablets | Green | IDT/O 15 | None
81140-103-10 | 30 mg | Round coated tablets | Blue | IDT/O 30 | None

Dispense in a tight, light-resistant container, with a child-resistant closure. Protect from moisture.

Store at controlled room temperature, 20°C to 25°C (68°F to 77°F), with excursions to 15°C to 30°C (59°F to 86°F).

Store ROXYBOND securely and dispose of properly.

17 PATIENT COUNSELING INFORMATION

Advise the patient to read the FDA-approved patient labeling (Medication Guide).

Storage and Disposal:

Because of the risks associated with accidental ingestion, misuse, and abuse, advise patients to store ROXYBOND securely, out of sight and reach of children, and in a location not accessible by others, including visitors to the home. Inform patients that leaving ROXYBOND unsecured can pose a deadly risk to others in the home [see Warnings and Precautions (5.1, 5.2), Drug Abuse and Dependence (9.2)] .

Advise patients and caregivers that when medicines are no longer needed, they should be disposed of promptly. Expired, unwanted, or unused ROXYBOND should be disposed of by flushing the unused medication down the toilet if a drug take-back option is not readily available. Inform patients that they can visit www.fda.gov/drugdisposal for a complete list of medicines recommended for disposal by flushing, as well as additional information on disposal of unused medicines.

Addiction, Abuse, and Misuse

Inform patients that the use of ROXYBOND, even when taken as recommended, can result in addiction, abuse, and misuse, which can lead to overdose and death [see Warnings and Precautions (5.1), Drug Abuse and Dependence (9.2)] . Instruct patients not to share ROXYBOND with others and to take steps to protect ROXYBOND from theft and misuse.

Life-Threatening Respiratory Depression

Inform patients of the risk of life-threatening respiratory depression, including information that the risk is greatest when starting ROXYBOND or when the dosage is increased, and that it can occur even at recommended dosages.

Educate patients and caregivers on how to recognize respiratory depression and emphasize the importance of calling 911 or getting emergency medical help right away in the event of a known or suspected overdose [see Warnings and Precautions (5.2), Overdosage (10)] .

Accidental Ingestion

Inform patients that accidental ingestion, especially by children, may result in respiratory depression or death [see Warnings and Precautions (5.2)] .

Interactions with Benzodiazepines and Other CNS Depressants

Inform patients and caregivers that potentially fatal additive effects may occur if ROXYBOND is used with benzodiazepines or other CNS depressants, including alcohol (e.g., non-benzodiazepine sedative/hypnotics, anxiolytics, tranquilizers, muscle relaxants, general anesthetics, antipsychotics, gabapentinoids [gabapentin or pregabalin], and other opioids), and not to use these concomitantly unless supervised by a healthcare provider [see Warnings and Precautions (5.3), Drug Interactions (7)] .

Patient Access to an Opioid Overdose Reversal Agent for the Emergency Treatment of Opioid Overdose

Inform patients and caregivers about opioid overdose reversal agents (e.g., naloxone, nalmefene). Discuss the importance of having access to an opioid overdose reversal agent, especially if the patient has risk factors for overdose (e.g., concomitant use of CNS depressants, a history of opioid use disorder, or prior opioid overdose) or if there are household members (including children) or other close contacts at risk for accidental ingestion or opioid overdose.

Discuss with the patient the options for obtaining an opioid overdose reversal agent (e.g., prescription, over-the-counter, or as part of a community-based program) [see Dosage and Administration (2.2), Warnings and Precautions (5.1, 5.3), Overdosage (10)] .

Educate patients and caregivers on how to recognize the signs and symptoms of an overdose.

Explain to patients and caregivers that effects of opioid overdose reversal agents like naloxone and nalmefene are temporary, and that they must call 911 or get emergency medical help right away in all cases of known or suspected opioid overdose, even if an opioid overdose reversal agent is administered [see Overdosage (10)] .

Advise patients and caregivers:

- how to treat with the overdose reversal agent in the event of an opioid overdose.
- to tell family and friends about their opioid overdose reversal agent, and to keep it in a place where family and friends can access it in an emergency.
- to read the Patient Information (or other educational material) that will come with their opioid overdose reversal agent. Emphasize the importance of doing this before an opioid emergency happens, so the patient and caregiver will know what to do.

Hyperalgesia and Allodynia

Inform patients and caregivers not to increase opioid dosage without first consulting a clinician. Advise patients to seek medical attention if they experience symptoms of hyperalgesia, including worsening pain, increased sensitivity to pain, or new pain [see Warnings and Precautions (5.7), Adverse Reactions (6.2)] .

Serotonin Syndrome

Inform patients that opioids could cause a rare but potentially life-threatening condition resulting from concomitant administration of serotonergic drugs. Warn patients of the symptoms of serotonin syndrome and to seek medical attention right away if symptoms develop. Instruct patients to inform their healthcare providers if they are taking, or plan to take serotonergic medication [see Drug Interactions (7)] .

MAOI Interaction

Inform patients to avoid taking ROXYBOND while using any drugs that inhibit monoamine oxidase. Patients should not start MAOIs while taking ROXYBOND [see Drug Interactions (7)] .

Important Administration Instructions

Instruct patients how to properly take ROXYBOND. Patients should be advised not to adjust the dose of ROXYBOND without consulting the prescribing healthcare provider [see Dosage and Administration (2), Warnings and Precautions (5.14)] .

Inform patients taking ROXYBOND that the medicine is absorbed by the body and the part of the tablet that contains inactive ingredients is eliminated from the body; patients may notice something that looks like a tablet in their stool.

Important Discontinuation Instructions

In order to avoid developing withdrawal symptoms, instruct patients not to discontinue ROXYBOND without first discussing a tapering plan with the prescriber [see Dosage and Administration (2.5)] .

Driving or Operating Machinery

Inform patients that ROXYBOND may impair the ability to perform potentially hazardous activities such as driving a car or operating dangerous machinery. Advise patients not to perform such tasks until they know how they will react to the medication [see Warnings and Precautions (5.15)] .

Constipation

Advise patients of the potential for severe constipation, including management instructions and when to seek medical attention [see Adverse Reactions (6.1), Clinical Pharmacology (12.2)] .

Healthcare professionals can telephone Protega Pharmaceuticals Inc. (1-844-798-3610) for information on this product.

Adrenal Insufficiency

Inform patients that opioids could cause adrenal insufficiency, a potentially life-threatening condition. Adrenal insufficiency may present with non-specific symptoms and signs such as nausea, vomiting, anorexia, fatigue, weakness, dizziness and low blood pressure. Advise patients to seek medical attention if they experience a constellation of these symptoms [see Warnings and Precautions (5.9)] .

Hypotension

Inform patients that ROXYBOND may cause orthostatic hypotension and syncope. Instruct patients how to recognize symptoms of low blood pressure and how to reduce the risk of serious consequences should hypotension occur (e.g., sit or lie down, carefully rise from sitting or lying position) [see Warnings and Precautions (5.10)] .

Anaphylaxis

Inform patients that anaphylaxis has been reported with ingredients contained in ROXYBOND. Advise patients how to recognize such a reaction and when to seek medical attention [see Contraindications (4), Adverse Reactions (6.2)] .

Pregnancy

Neonatal Opioid Withdrawal Syndrome

Inform female patients of reproductive potential that use of ROXYBOND for an extended period of time during pregnancy can result in neonatal opioid withdrawal syndrome, which may be life-threatening if not recognized and treated [see Warnings and Precautions (5.4), Use in Specific Populations (8.1)] .

Embryo-Fetal Toxicity

Inform female patients of reproductive potential that ROXYBOND can cause fetal harm and to inform their healthcare provider of a known or suspected pregnancy [see Use in Specific Populations (8.1)] .

Lactation

Advise breastfeeding women using ROXYBOND to carefully observe infants for increased sleepiness (more than usual), breathing difficulties, or limpness. Instruct breastfeeding women to seek immediate medical care if they notice these signs [see Use in Specific Populations (8.2)] .

Infertility

Inform patients that use of opioids for an extended period of time may cause reduced fertility. It is not known whether these effects on fertility are reversible [see Use in Specific Populations (8.3)] .

Manufactured for: Protega Pharmaceuticals Inc.
Princeton, NJ 08540
(C) 2025, Protega Pharmaceuticals Inc.
GK-425

Medication Guide
ROXYBOND (\'räk-sē- ‘bänd\)
(oxycodone hydrochloride) tablets USP, CII

ROXYBOND is:

- A strong prescription pain medicine that contains an opioid (narcotic) that is used to manage pain severe enough to require an opioid pain medicine, when other pain treatments such as non-opioid pain medicines do not treat your pain well enough or you cannot tolerate them.
- An opioid pain medicine that can put you at risk for overdose and death. Even if you take your dose correctly as prescribed you are at risk for opioid addiction, abuse, and misuse that can lead to death.

Important information about ROXYBOND:

- Get emergency help or call 911 right away if you take too much ROXYBOND (overdose).When you first start taking ROXYBOND, when your dose is changed, or if you take too much (overdose), serious or life-threatening breathing problems that can lead to death may occur. Ask your healthcare provider about medicines like naloxone or nalmefene that can be used in an emergency to reverse an opioid overdose.
- Taking ROXYBOND with other opioid medicines, benzodiazepines, gabapentinoids (gabapentin or pregabalin), alcohol, or other central nervous system depressants (including street drugs) can cause severe drowsiness, decreased awareness, breathing problems, coma, and death.
- Never give anyone else your ROXYBOND. They could die from taking it. Selling or giving away ROXYBOND is against the law.
- Store ROXYBOND securely, out of sight and reach of children and in a location not accessible by others, including visitors to the home.

Do not take ROXYBOND if you have:

- severe asthma, trouble breathing, or other lung problems.
- a bowel blockage or have narrowing of the stomach or intestines.
- allergy to oxycodone.

Before taking ROXYBOND, tell your healthcare provider if you have a history of:

- head injury, seizures
- problems urinating

- liver, kidney, thyroid problems
- pancreas or gallbladder problems

- abuse of street or prescription drugs, alcohol addiction, opioid overdose or mental health problems.

Tell your healthcare provider if you are:

- noticing your pain getting worse.If your pain gets worse after you take ROXYBOND, do not take more of ROXYBOND without first talking to your healthcare provider. Talk to your healthcare provider if the pain that you have increases, if you feel more sensitive to pain, or if you have new pain after taking ROXYBOND.
- pregnant or planning to become pregnant.Use of ROXYBOND for an extended period of time during pregnancy can cause withdrawal symptoms in your newborn baby that could be life-threatening if not recognized and treated.
- breastfeeding.ROXYBOND passes into breast milk and may harm your baby. Carefully observe infants for increased sleepiness (more than usual), breathing difficulties, or limpness. Seek immediate medical care if you notice these signs.
- Living in a household where there are small children or someone who has abused street or prescription drugs.
- taking prescription or over-the-counter medicines, vitamins, or herbal supplements. Taking ROXYBOND with certain other medicines can cause serious side effects that could lead to death.

When taking ROXYBOND:

- Do not change your dose. Take ROXYBOND exactly as prescribed by your healthcare provider. Use the lowest dose possible for the shortest time needed.
- For acute (short-term) pain, you may only need to take ROXYBOND for a few days. You may have some ROXYBOND left over that you did not use. See disposal information at the bottom of this section for directions on how to safely throw away (dispose of) your unused ROXYBOND.
- Take your prescribed dose every 4 to 6 hours as needed for pain. Do not take more than your prescribed dose. If you miss a dose, take your next dose at your usual time.
- Call your healthcare provider if the dose you are taking does not control your pain.
- If you have been taking ROXYBOND regularly, do not stop taking ROXYBOND without talking to your healthcare provider.
- Dispose of expired, unwanted, or unused ROXYBOND by promptly flushing down the toilet, if a drug take-back option is not readily available. Visit www.fda.gov/drugdisposal for additional information on disposal of unused medicines.

While taking ROXYBOND DO NOT:

- Drive or operate heavy machinery, until you know how ROXYBOND affects you. ROXYBOND can make you sleepy, dizzy, or lightheaded.
- Drink alcohol or use prescription or over-the-counter medicines that contain alcohol. Using products containing alcohol during treatment with ROXYBOND may cause you to overdose and die.

The possible side effects of ROXYBOND are:

- constipation, nausea, sleepiness, vomiting, tiredness, headache, dizziness, abdominal pain. Call your healthcare provider if you have any of these symptoms and they are severe.

Get emergency medical help or call 911 right away if you have:

- trouble breathing, shortness of breath, fast heartbeat, chest pain, swelling of your face, tongue, or throat, extreme drowsiness, light-headedness when changing positions, feeling faint, agitation, high body temperature, trouble walking, stiff muscles, or mental changes such as confusion.

These are not all the possible side effects of ROXYBOND. Call your healthcare provider for medical advice about side effects. You may report side effects to the FDA at 1-800-FDA-1088. For more information go to dailymed.nlm.nih.gov
Manufactured for: Protega Pharmaceuticals Inc.

This Medication Guide has been approved by the U.S. Food and Drug Administration.

Issued: December 2025

GK-426

Principal Display Panel – 5 mg Bottle Label

NDC81140-101-10 100 Tablets

RoxyBond™CII

(oxycodone hydrochloride)
Tablets
5 mg

Rx Only

Attention Dispenser:Accompanying Medication Guide
must be provided to the patient upon dispensing.

Manufactured for:
Protega Pharmaceuticals, Inc.
Princeton, NJ 08540

Principal Display Panel – 15 mg Bottle Label

NDC81140-102-10 100 Tablets

RoxyBond™CII

(oxycodone hydrochloride)
Tablets
15 mg

Rx Only

Attention Dispenser:Accompanying Medication Guide
must be provided to the patient upon dispensing.

Manufactured for:
Protega Pharmaceuticals, Inc.
Princeton, NJ 08540

Principal Display Panel – 30 mg Bottle Label

NDC81140-103-10 100 Tablets

RoxyBond™CII

(oxycodone hydrochloride)
Tablets
30 mg

Rx Only

Attention Dispenser:Accompanying Medication Guide
must be provided to the patient upon dispensing.

Manufactured for:
Protega Pharmaceuticals, Inc.
Princeton, NJ 08540

Principal Display Panel – 10 mg Bottle Label

NDC81140-104-10 100 Tablets

RoxyBond™CII

(oxycodone hydrochloride)
Tablets
10 mg

Rx Only

Attention Dispenser:Accompanying Medication Guide
must be provided to the patient upon dispensing.

Manufactured for:
Protega Pharmaceuticals, Inc.
Princeton, NJ 08540